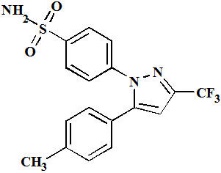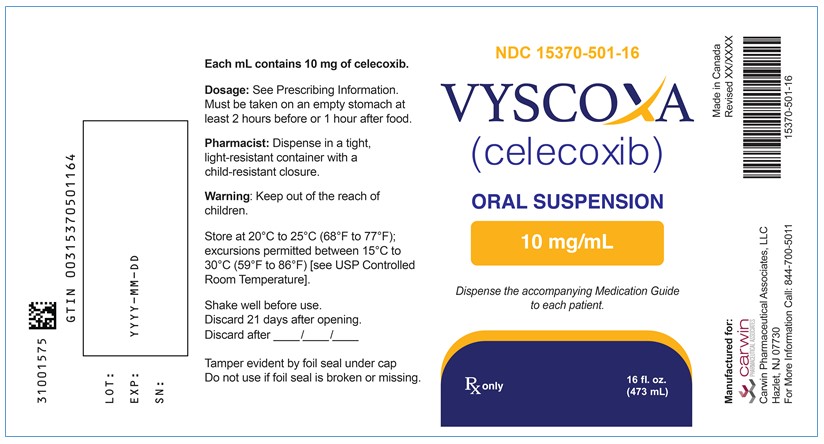 DRUG LABEL: VYSCOXA
NDC: 15370-501 | Form: Suspension
Manufacturer: Carwin Pharmaceutical Associates, LLC
Category: prescription | Type: HUMAN PRESCRIPTION DRUG LABEL
Date: 20250731

ACTIVE INGREDIENTS: CELECOXIB 10 mg/1 mL
INACTIVE INGREDIENTS: ANHYDROUS CITRIC ACID; GLYCERIN; SILODRATE; METHYLPARABEN; PROPYLPARABEN; TRISODIUM CITRATE DIHYDRATE; SUCRALOSE; XANTHAN GUM; WATER

HIGHLIGHTS OF PRESCRIBING INFORMATION

These highlights do not include all the information needed to use VYSCOXA safely and effectively. See full prescribing information for VYSCOXA.
VYSCOXA TM (celecoxib) oral suspension, Initial U.S. Approval: 1998

WARNING: RISK OF SERIOUS CARDIOVASCULAR AND GASTROINTESTINAL EVENTS

See full prescribing information for complete boxed warning.

- Nonsteroidal anti-inflammatory drugs (NSAIDs) cause an increased risk of serious cardiovascular thrombotic events, including myocardial infarction and stroke, which can be fatal. This risk may occur early in the treatment and may increase with duration of use. (5.1)
- VYSCOXA is contraindicated in the setting of coronary artery bypass graft (CABG) surgery. (4, 5.1)
- NSAIDs cause an increased risk of serious gastrointestinal (GI) adverse events including bleeding, ulceration, and perforation of the stomach or intestines, which can be fatal. These events can occur at any time during use and without warning symptoms. Elderly patients and patients with a prior history of peptic ulcer disease and/or GI bleeding are at greater risk for serious GI events. (5.2)

1. INDICATIONS AND USAGE

VYSCOXA contains celecoxib, a nonsteroidal anti-inflammatory drug, and is indicated:

In adults for

- Osteoarthritis (OA) (1.1)
- Rheumatoid Arthritis (RA) (1.2)
- Ankylosing Spondylitis (AS) (1.3)

In pediatric patients two years and older for

- Juvenile Rheumatoid Arthritis (JRA) (1.4)

Limitations of Use

VYSCOXA must be administered on an empty stomach at least 2 hours before or 1 hour after food. Taking VYSCOXA with food results in plasma exposures of celecoxib up to 50% higher than intended. If patients cannot tolerate VYSCOXA in the fasted state, discontinue use of VYSCOXA (2.1, 5, 12)

2. DOSAGE AND ADMINISTRATION

- Use the lowest effective dosage for shortest duration consistent with individual patient treatment goals. (2.1)
- OA: 200 mg (20 mL) once daily or 100 mg (10 mL) twice daily. (2.2, 14.1)
- RA: 100 mg (10 mL) to 200 mg (20 mL) twice daily. (2.3, 14.2)
- AS: 200 mg (20 mL) once daily single dose or 100 mg (10 mL) twice daily. If no effect is observed after 6 weeks, a trial of 200 mg (20 mL) twice daily may be of benefit. (2.4, 14.3)
- JRA: 50 mg (5 mL) twice daily in patients 10 kg to 25 kg. 100 mg (10 mL) twice daily in patients more than 25 kg. (2.5, 14.4)

Important:VYSCOXA is not recommended at a single dose greater than 200 mg (20 mL). Single doses of the suspension greater than 200 mg (20 mL) may result in celecoxib concentrations higher than expected. For patients who require a single dose over 200 mg (20 mL), use a different celecoxib formulation (2.1, 12.3)

Hepatic Impairment: Reduce daily dose by 50% in patients with moderate hepatic impairment (Child-Pugh Class B). (2.6, 8.6, 12.3)

Poor Metabolizers of CYP2C9 Substrates: Consider a dose reduction by 50% (or alternative management for JRA) in patients who are known or suspected to be CYP2C9 poor metabolizers. (2.6, 8.8, 12.3).

3. DOSAGE FORMS AND STRENGTHS

Oral suspension: 10 mg/mL (3)

4. CONTRAINDICATIONS

- Known hypersensitivity to celecoxib, or any components of the drug product or sulfonamides. (4)
- History of asthma, urticaria, or other allergic-type reactions after taking aspirin or other NSAIDs. (4)
- In the setting of CABG surgery. (4)

5. WARNINGS AND PRECAUTIONS

- Hepatotoxicity: Inform patients of warning signs and symptoms of hepatotoxicity. Discontinue if abnormal liver tests persist or worsen or if clinical signs and symptoms of liver disease develop. (5.3)
- Hypertension: Patients taking some antihypertensive medications may have impaired response to these therapies when taking NSAIDs. Monitor blood pressure. (5.4, 7)
- Heart Failure and Edema: Avoid use of VYSCOXA in patients with severe heart failure unless benefits are expected to outweigh risk of worsening heart failure. (5.5)
- Renal Toxicity: Monitor renal function in patients with renal or hepatic impairment, heart failure, dehydration, or hypovolemia. Avoid use of VYSCOXA in patients with advanced renal disease unless benefits are expected to outweigh risk of worsening renal function. (5.6)
- Anaphylactic Reactions: Seek emergency help if an anaphylactic reaction occurs. (5.7)
- Exacerbation of Asthma Related to Aspirin Sensitivity: VYSCOXA is contraindicated in patients with aspirin-sensitive asthma. Monitor patients with preexisting asthma (without aspirin sensitivity). (5.8)
- Serious Skin Reactions: Discontinue VYSCOXA at first appearance of skin rash or other signs of hypersensitivity. (5.9)
- Drug Reaction with Eosinophilia and Systemic Symptoms (DRESS): Discontinue and evaluate clinically. (5.10)
- Fetal Toxicity: Limit use of NSAIDs, including VYSCOXA, between about 20 to 30 weeks in pregnancy due to the risk of oligohydramnios/fetal renal dysfunction. Avoid use of NSAIDs in women at about 30 weeks gestation and later in pregnancy due to the risks of oligohydramnios/fetal renal dysfunction and premature closure of the fetal ductus arteriosus. (5.11, 8.1)
- Hematologic Toxicity: Monitor hemoglobin or hematocrit in patients with any signs or symptoms of anemia. (5.12, 7)

6. ADVERSE REACTIONS

Most common adverse reactions in arthritis trials (>2% and >placebo) are: abdominal pain, diarrhea, dyspepsia, flatulence, peripheral edema, accidental injury, dizziness, pharyngitis, rhinitis, sinusitis, upper respiratory tract infection, rash. (6.1)

To report SUSPECTED ADVERSE REACTIONS, contact Carwin Pharmaceutical Associates, LLC at 1-844-700-5011 or FDA at 1-800-FDA-1088 or www.fda.gov/medwatch.

7. DRUG INTERACTIONS

- Drugs that Interfere with Hemostasis (e.g., warfarin, aspirin, selective serotonin reuptake inhibitors [SSRIs]/serotonin norepinephrine reuptake inhibitors [SNRIs]): Monitor patients for bleeding who are concomitantly taking VYSCOXA with drugs that interfere with hemostasis. Concomitant use of VYSCOXA and analgesic doses of aspirin is not generally recommended. (7)
- Angiotensin Converting Enzyme (ACE) Inhibitors, Angiotensin Receptor Blockers (ARB), or Beta-Blockers: Concomitant use with VYSCOXA may diminish the antihypertensive effect of these drugs. Monitor blood pressure. (7)
- ACE Inhibitors and ARBs: Concomitant use with VYSCOXA in elderly, volume depleted, or those with renal impairment may result in deterioration of renal function. In such high risk patients, monitor for signs of worsening renal function. (7)
- Diuretics: NSAIDs can reduce natriuretic effect of furosemide and thiazide diuretics. Monitor patients to assure diuretic efficacy including antihypertensive effects. (7)
- Digoxin: Concomitant use with VYSCOXA can increase serum concentration and prolong half-life of digoxin. Monitor serum digoxin levels. (7)

8. USE IN SPECIFIC POPULATIONS

Infertility: NSAIDs are associated with reversible infertility. Consider withdrawal of VYSCOXA in women who have difficulties conceiving. (8.3)

FULL PRESCRIBING INFORMATION

WARNING: RISK OF SERIOUS CARDIOVASCULAR AND GASTROINTESTINAL EVENTS

Cardiovascular Thrombotic Events

- Nonsteroidal anti-inflammatory drugs (NSAIDs) cause an increased risk of serious cardiovascular thrombotic events, including myocardial infarction, and stroke, which can be fatal. This risk may occur early in the treatment and may increase with duration of use [see Warnings and Precautions (5.1)].
- VYSCOXA is contraindicated in the setting of coronary artery bypass graft (CABG) surgery [see Contraindications (4) and Warnings and Precautions (5.1)].

Gastrointestinal Bleeding, Ulceration, and Perforation

- NSAIDs cause an increased risk of serious gastrointestinal (GI) adverse events including bleeding, ulceration, and perforation of the stomach or intestines, which can be fatal. These events can occur at any time during use and without warning symptoms. Elderly patients and patients with a prior history of peptic ulcer disease and/or GI bleeding are at greater risk for serious GI events [see Warnings and Precautions (5.2)].

1. INDICATIONS AND USAGE

VYSCOXA is indicated

In adults for the management of the signs and symptoms of:

1.1 Osteoarthritis

(OA) [see Clinical Studies (14.1)].

1.2 Rheumatoid Arthritis

(RA) [see Clinical Studies (14.2)].

1.3 Ankylosing Spondylitis

(AS) [see Clinical Studies (14.3)].

In pediatric patients two years of age and older for the management of the signs and symptoms of:

1.4 Juvenile Rheumatoid Arthritis

(JRA) [see Clinical Studies (14.4)].

Limitations of Use
VYSCOXA must be administered on an empty stomach at least 2 hours before or 1 hour after food. Taking VYSCOXA with food results in plasma exposures of celecoxib up to 50% higher than intended. If patients cannot tolerate VYSCOXA in the fasted state, discontinue use of VYSCOXA (reference Sections 2.1 , 5, 12).

VYSCOXA is NOT indicated for the management of acute pain or treatment of primary dysmenorrhea.

2. DOSAGE AND ADMINISTRATION

2.1 General Dosing Instructions

Carefully consider the potential benefits and risks of VYSCOXA and other treatment options before deciding to use VYSCOXA. Use the lowest effective dosage for the shortest duration consistent with individual patient treatment goals [see Warnings and Precautions (5)].

The maximum single dose of VYSCOXA is 200 mg (20 mL). Administering more than 200 mg (20 mL) in a single dose of the VYXCOXA suspension may result in higher than intended plasma concentrations of celecoxib. In patients requiring a single dose greater than 200 mg (20 mL), use a different product.

VYSCOXA must be taken on an empty stomach at least 2 hours before or 1 hour after food [see Clinical Pharmacology (12.3)].

For patients who cannot tolerate dosing with VYSCOXA on an empty stomach, discontinue the use of this product. Do not advise the patient to take VYSCOXA with food.

2.2 Osteoarthritis

For OA, the dosage is 200 mg (20 mL) per day administered as a single dose or as 100 mg (10 mL) twice daily.

2.3 Rheumatoid Arthritis

For RA, the dosage is 100 mg (10 mL) to 200 mg (20 mL) twice daily.

2.4 Ankylosing Spondylitis

For AS, the dosage is 200 mg (20 mL) daily in single (once per day) dose or 100 mg (10 mL) twice daily. If no effect is observed after 6 weeks, a trial of 200 mg (20 mL) twice daily may be worthwhile. If no effect is observed after 6 weeks on 200 mg (20 mL) twice daily, a response is not likely and consideration should be given to alternate treatment options.

2.5 Juvenile Rheumatoid Arthritis

For JRA, the dosage for pediatric patients (age 2 years and older) is based on weight. For patients weighing 10 kg to 25 kg the recommended dose is 50 mg (5 mL) twice daily. For patients greater than 25 kg the recommended dose is 100 mg (10 mL) twice daily.

2.6 Special Populations

Hepatic Impairment

In patients with moderate hepatic impairment (Child-Pugh Class B), reduce the dose by 50%. The use of VYSCOXA in patients with severe hepatic impairment is not recommended [see Warnings and Precautions (5.3), Use in Specific Populations (8.6), and Clinical Pharmacology (12.3)].

Poor Metabolizers of CYP2C9 Substrates

In adult patients who are known or suspected to be poor CYP2C9 metabolizers based on genotype or previous history/experience with other CYP2C9 substrates (such as warfarin, phenytoin), initiate treatment with half of the lowest recommended dose.

In patients with JRA who are known or suspected to be poor CYP2C9 metabolizers, consider using alternative treatments [see Use in Specific populations (8.8) and Clinical Pharmacology (12.5)].

3. DOSAGE FORMS AND STRENGTHS

Oral suspension: 10 mg/mL of celecoxib as a white, opaque, unflavored suspension.

4. CONTRAINDICATIONS

VYSCOXA is contraindicated in the following patients:

- Known hypersensitivity (e.g., anaphylactic reactions and serious skin reactions) to celecoxib, any components of the drug product [see Warnings and Precautions (5.7, 5.9)].
- History of asthma, urticaria, or other allergic-type reactions after taking aspirin or other NSAIDs. Severe, sometimes fatal, anaphylactic reactions to NSAIDs, have been reported in such patients [see Warnings and Precautions (5.7, 5.8)].
- In the setting of CABG surgery [see Warnings and Precautions (5.1)].
- In patients who have demonstrated allergic-type reactions to sulfonamides [see Warnings and Precautions (5.7)].

5. WARNINGS AND PRECAUTIONS

5.1 Cardiovascular Thrombotic Events

Clinical trials of several cyclooxygenase-2 (COX-2) selective and nonselective NSAIDs of up to three years duration have shown an increased risk of serious cardiovascular (CV) thrombotic events, including myocardial infarction (MI) and stroke, which can be fatal. Based on available data, it is unclear that the risk for CV thrombotic events is similar for all NSAIDs. The relative increase in serious CV thrombotic events over baseline conferred by NSAID use appears to be similar in those with and without known CV disease or risk factors for CV disease. However, patients with known CV disease or risk factors had a higher absolute incidence of excess serious CV thrombotic events, due to their increased baseline rate. Some observational studies found that this increased risk of serious CV thrombotic events began as early as the first weeks of treatment. The increase in CV thrombotic risk has been observed most consistently at higher doses.

In the APC (Adenoma Prevention with Celecoxib) trial, there was about a threefold increased risk of the composite endpoint of cardiovascular death, MI, or stroke for the celecoxib 400 mg twice daily and celecoxib 200 mg twice daily treatment arms compared to placebo. The increases in both celecoxib dose groups versus placebo-treated patients were mainly due to an increased incidence of myocardial infarction [see Clinical Studies (14.6)].

A randomized controlled trial entitled the Prospective Randomized Evaluation of Celecoxib Integrated Safety vs. Ibuprofen Or Naproxen (PRECISION) was conducted to assess the relative cardiovascular thrombotic risk of a COX-2 inhibitor, celecoxib, compared to the non-selective NSAIDs naproxen and ibuprofen. Celecoxib 100 mg twice daily was non-inferior to naproxen 375 to 500 mg twice daily and ibuprofen 600 to 800 mg three times daily for the composite endpoint of the Antiplatelet Trialists' Collaboration (APTC), which consists of cardiovascular death (including hemorrhagic death), non-fatal myocardial infarction, and non-fatal stroke [see Clinical Studies (14.5)].

To minimize the potential risk for an adverse CV event in NSAID-treated patients, use the lowest effective dose for the shortest duration possible. Physicians and patients should remain alert for the development of such events, throughout the entire treatment course, even in the absence of previous CV symptoms. Patients should be informed about the symptoms of serious CV events and the steps to take if they occur.

There is no consistent evidence that concurrent use of aspirin mitigates the increased risk of serious CV thrombotic events associated with NSAID use. The concurrent use of aspirin and an NSAID, such as celecoxib, increases the risk of serious gastrointestinal (GI) events [see Warnings and Precautions (5.2)].

Status Post Coronary Artery Bypass Graft (CABG) Surgery

Two large controlled clinical trials of a COX-2 selective NSAID for the treatment of pain in the first 10 to 14 days following CABG surgery found an increased incidence of myocardial infarction and stroke. NSAIDs are contraindicated in the setting of CABG [see Contraindications (4)].

Post-MI Patients

Observational studies conducted in the Danish National Registry have demonstrated that patients treated with NSAIDs in the post-MI period were at increased risk of reinfarction, CV-related death, and all-cause mortality beginning in the first week of treatment. In this same cohort, the incidence of death in the first year post-MI was 20 per 100 person years in NSAID-treated patients compared to 12 per 100 person years in non-NSAID exposed patients. Although the absolute rate of death declined somewhat after the first year post-MI, the increased relative risk of death in NSAID users persisted over at least the next four years of follow-up.

Avoid the use of VYSCOXA in patients with a recent MI unless the benefits are expected to outweigh the risk of recurrent CV thrombotic events. If VYSCOXA is used in patients with a recent MI, monitor patients for signs of cardiac ischemia.

5.2 Gastrointestinal Bleeding, Ulceration, and Perforation

NSAIDs, including celecoxib cause serious gastrointestinal (GI) adverse events including inflammation, bleeding, ulceration, and perforation of the esophagus, stomach, small intestine, or large intestine, which can be fatal. These serious adverse events can occur at any time, with or without warning symptoms, in patients treated with VYSCOXA. Only one in five patients who develop a serious upper GI adverse event on NSAID therapy is symptomatic. Upper GI ulcers, gross bleeding, or perforation caused by NSAIDs occurred in approximately 1% of patients treated for 3 to 6 months, and in about 2% to 4% of patients treated for one year. However, even short-term NSAID therapy is not without risk.

Risk Factors for GI Bleeding, Ulceration, and Perforation

Patients with a prior history of peptic ulcer disease and/or GI bleeding who used NSAIDs had a greater than 10-fold increased risk for developing a GI bleed compared to patients without these risk factors. Other factors that increase the risk of GI bleeding in patients treated with NSAIDs include longer duration of NSAID therapy; concomitant use of oral corticosteroids, antiplatelet drugs (such as aspirin), anticoagulants; or selective serotonin reuptake inhibitors (SSRIs); smoking; use of alcohol; older age; and poor general health status. Most postmarketing reports of fatal GI events occurred in elderly or debilitated patients. Additionally, patients with advanced liver disease and/or coagulopathy are at increased risk for GI bleeding.

Complicated and symptomatic ulcer rates were 0.78% at nine months for all patients in the CLASS trial, and 2.19% for the subgroup on low-dose ASA. Patients 65 years of age and older had an incidence of 1.40% at nine months, 3.06% when also taking ASA [see Clinical Studies (14.6)].

Strategies to Minimize the GI Risks in NSAID-treated patients:

- Use the lowest effective dosage for the shortest possible duration.
- Avoid administration of more than one NSAID at a time.
- Avoid use in patients at higher risk unless benefits are expected to outweigh the increased risk of bleeding. For such patients, as well as those with active GI bleeding, consider alternate therapies other than NSAIDs.
- Remain alert for signs and symptoms of GI ulceration and bleeding during NSAID therapy.
- If a serious GI adverse event is suspected, promptly initiate evaluation and treatment, and discontinue VYSCOXA until a serious GI adverse event is ruled out.
- In the setting of concomitant use of low-dose aspirin for cardiac prophylaxis, monitor patients more closely for evidence of GI bleeding [see Drug Interactions (7)].

5.3 Hepatotoxicity

Elevations of ALT or AST (three or more times the upper limit of normal [ULN]) have been reported in approximately 1% of NSAID-treated patients in clinical trials. In addition, rare, sometimes fatal, cases of severe hepatic injury, including fulminant hepatitis, liver necrosis, and hepatic failure have been reported.

Elevations of ALT or AST (less than three times ULN) may occur in up to 15% of patients treated with NSAIDs including celecoxib.

In controlled clinical trials of celecoxib, the incidence of borderline elevations (greater than or equal to 1.2 times and less than 3 times the upper limit of normal) of liver associated enzymes was 6% for celecoxib and 5% for placebo, and approximately 0.2% of patients taking celecoxib and 0.3% of patients taking placebo had notable elevations of ALT and AST.

Inform patients of the warning signs and symptoms of hepatotoxicity (e.g., nausea, fatigue, lethargy, diarrhea, pruritus, jaundice, right upper quadrant tenderness, and "flu-like" symptoms). If clinical signs and symptoms consistent with liver disease develop, or if systemic manifestations occur (e.g., eosinophilia, rash), discontinue VYSCOXA immediately, and perform a clinical evaluation of the patient.

5.4 Hypertension

NSAIDs, including VYSCOXA, can lead to new onset of hypertension or worsening of preexisting hypertension, either of which may contribute to the increased incidence of CV events. Patients taking angiotensin converting enzyme (ACE) inhibitors, thiazide diuretics or loop diuretics may have impaired response to these therapies when taking NSAIDs [see Drug Interactions (7)].

See Clinical Studies (14.5, 14.6) for additional blood pressure data for VYSCOXA.

Monitor blood pressure (BP) during the initiation of NSAID treatment and throughout the course of therapy.

5.5 Heart Failure and Edema

The Coxib and traditional NSAID Trialists' Collaboration meta-analysis of randomized controlled trials demonstrated an approximately two-fold increase in hospitalizations for heart failure in COX-2 selective-treated patients and nonselective NSAID-treated patients compared to placebo-treated patients. In a Danish National Registry study of patients with heart failure, NSAID use increased the risk of MI, hospitalization for heart failure, and death.

Additionally, fluid retention and edema have been observed in some patients treated with NSAIDs. Use of celecoxib may blunt the CV effects of several therapeutic agents used to treat these medical conditions (e.g., diuretics, ACE inhibitors, or angiotensin receptor blockers [ARBs]) [see Drug Interactions (7)].

In the CLASS study [see Clinical Studies (14.6)], the Kaplan-Meier cumulative rates at 9 months of peripheral edema in patients on celecoxib 400 mg twice daily (4-fold and 2-fold the recommended OA and RA doses, respectively), ibuprofen 800 mg three times daily and diclofenac 75 mg twice daily were 4.5%, 6.9% and 4.7%, respectively.

Avoid the use of VYSCOXA in patients with severe heart failure unless the benefits are expected to outweigh the risk of worsening heart failure. If VYSCOXA is used in patients with severe heart failure, monitor patients for signs of worsening heart failure.

5.6 Renal Toxicity and Hyperkalemia

Renal Toxicity

Long-term administration of NSAIDs has resulted in renal papillary necrosis and other renal injury.

Renal toxicity has also been seen in patients in whom renal prostaglandins have a compensatory role in the maintenance of renal perfusion. In these patients, administration of an NSAID may cause a dose-dependent reduction in prostaglandin formation and, secondarily, in renal blood flow, which may precipitate overt renal decompensation. Patients at greatest risk of this reaction are those with impaired renal function, dehydration, hypovolemia, heart failure, liver dysfunction, those taking diuretics, ACE inhibitors or the ARBs, and the elderly. Discontinuation of NSAID therapy is usually followed by recovery to the pretreatment state.

No information is available from controlled clinical studies regarding the use of celecoxib in patients with advanced renal disease. The renal effects of celecoxib may hasten the progression of renal dysfunction in patients with preexisting renal disease.

Correct volume status in dehydrated or hypovolemic patients prior to initiating VYSCOXA. Monitor renal function in patients with renal or hepatic impairment, heart failure, dehydration, or hypovolemia during use of VYSCOXA [see Drug Interactions (7)]. Avoid the use of VYSCOXA in patients with advanced renal disease unless the benefits are expected to outweigh the risk of worsening renal function. If VYSCOXA is used in patients with advanced renal disease, monitor patients for signs of worsening renal function.

Hyperkalemia

Increases in serum potassium concentration, including hyperkalemia, have been reported with use of NSAIDs, even in some patients without renal impairment. In patients with normal renal function, these effects have been attributed to a hyporeninemic- hypoaldosteronism state.

5.7 Anaphylactic Reactions

Celecoxib has been associated with anaphylactic reactions in patients with and without known hypersensitivity to celecoxib and in patients with aspirin sensitive asthma. Celecoxib is a sulfonamide and both NSAIDs and sulfonamides may cause allergic type reactions including anaphylactic symptoms and life-threatening or less severe asthmatic episodes in certain susceptible people [see Contraindications (4) and Warnings and Precautions (5.8)].

Seek emergency help if any anaphylactic reaction occurs.

5.8 Exacerbation of Asthma Related to Aspirin Sensitivity

A subpopulation of patients with asthma may have aspirin-sensitive asthma which may include chronic rhinosinusitis complicated by nasal polyps; severe, potentially fatal bronchospasm; and/or intolerance to aspirin and other NSAIDs. Because cross-reactivity between aspirin and other NSAIDs has been reported in such aspirin-sensitive patients, VYSCOXA is contraindicated in patients with this form of aspirin sensitivity [see Contraindications (4)]. When VYSCOXA is used in patients with preexisting asthma (without known aspirin sensitivity), monitor patients for changes in the signs and symptoms of asthma.

5.9 Serious Skin Reactions

Serious skin reactions have occurred following treatment with celecoxib, including erythema multiforme, exfoliative dermatitis, Stevens-Johnson Syndrome (SJS), toxic epidermal necrolysis (TEN), drug reaction with eosinophilia and systemic symptoms (DRESS), acute generalized exanthematous pustulosis (AGEP), and fixed drug eruption (FDE) which may present as a more severe variant known as generalized bullous fixed drug eruption (GBFDE). These serious events may occur without warning and can be fatal.

Inform patients about the signs and symptoms of serious skin reactions, and to discontinue the use of VYSCOXA at the first appearance of skin rash or any other sign of hypersensitivity. VYSCOXA is contraindicated in patients with previous serious skin reactions to NSAIDs [see Contraindications (4)].

5.10 Drug Reaction with Eosinophilia and Systemic Symptoms (DRESS)

Drug Reaction with Eosinophilia and Systemic Symptoms (DRESS) has been reported in patients taking NSAIDs such as celecoxib. Some of these events have been fatal or life-threatening. DRESS typically, although not exclusively, presents with fever, rash, lymphadenopathy, and/or facial swelling. Other clinical manifestations may include hepatitis, nephritis, hematological abnormalities, myocarditis, or myositis. Sometimes symptoms of DRESS may resemble an acute viral infection. Eosinophilia is often present. Because this disorder is variable in its presentation, other organ systems not noted here may be involved. It is important to note that early manifestations of hypersensitivity, such as fever or lymphadenopathy, may be present even though rash is not evident. If such signs or symptoms are present, discontinue VYSCOXA and evaluate the patient immediately.

5.11 Fetal Toxicity

Premature Closure of Fetal Ductus Arteriosus

Avoid use of NSAIDs, including VYSCOXA, in pregnant women at about 30 weeks gestation and later. NSAIDs, including VYSCOXA, increase the risk of premature closure of the fetal ductus arteriosus at approximately this gestational age.

Oligohydramnios/Neonatal Renal Impairment

Use of NSAIDs, including VYSCOXA, at about 20 weeks gestation or later in pregnancy may cause fetal renal dysfunction leading to oligohydramnios and, in some cases, neonatal renal impairment. These adverse outcomes are seen, on average, after days to weeks of treatment, although oligohydramnios has been infrequently reported as soon as 48 hours after NSAID initiation. Oligohydramnios is often, but not always, reversible with treatment discontinuation. Complications of prolonged oligohydramnios may, for example, include limb contractures and delayed lung maturation. In some postmarketing cases of impaired neonatal renal function, invasive procedures such as exchange transfusion or dialysis were required.

If NSAID treatment is necessary between about 20 weeks and 30 weeks gestation, limit VYSCOXA use to the lowest effective dose and shortest duration possible. Consider ultrasound monitoring of amniotic fluid if VYSCOXA treatment extends beyond 48 hours. Discontinue VYSCOXA if oligohydramnios occurs and follow up according to clinical practice [see Use in Specific Populations (8.1)].

5.12 Hematological Toxicity

Anemia has occurred in NSAID-treated patients. This may be due to occult or gross blood loss, fluid retention, or an incompletely described effect on erythropoiesis. If a patient treated with VYSCOXA has any signs or symptoms of anemia, monitor hemoglobin or hematocrit.

In controlled clinical trials the incidence of anemia was 0.6% with celecoxib and 0.4% with placebo. Patients on long-term treatment with VYSCOXA should have their hemoglobin or hematocrit checked if they exhibit any signs or symptoms of anemia or blood loss.

NSAIDs, including VYSCOXA, may increase the risk of bleeding events. Co-morbid conditions such as coagulation disorders or concomitant use of warfarin, other anticoagulants, antiplatelet drugs (e.g., aspirin), SSRIs and serotonin norepinephrine reuptake inhibitors (SNRIs) may increase this risk. Monitor these patients for signs of bleeding [see Drug Interactions (7)].

5.13 Masking of Inflammation and Fever

The pharmacological activity of VYSCOXA in reducing inflammation, and possibly fever, may diminish the utility of diagnostic signs in detecting infections.

5.14 Laboratory Monitoring

Because serious GI bleeding, hepatotoxicity, and renal injury can occur without warning symptoms or signs, consider monitoring patients on long-term NSAID treatment with a CBC and a chemistry profile periodically [see Warnings and Precautions (5.2, 5.3, 5.6)].

In controlled clinical trials, elevated BUN occurred more frequently in patients receiving celecoxib compared with patients on placebo. This laboratory abnormality was also seen in patients who received comparator NSAIDs in these studies. The clinical significance of this abnormality has not been established.

5.15 Disseminated Intravascular Coagulation (DIC)

Because of the risk of disseminated intravascular coagulation with use of VYSCOXA in pediatric patients with systemic onset JRA, monitor patients for signs and symptoms of abnormal clotting or bleeding, and inform patients and their caregivers to report symptoms as soon as possible.

6. ADVERSE REACTIONS

The following adverse reactions are discussed in greater detail in other sections of the labeling:

- Cardiovascular Thrombotic Events [see Warnings and Precautions (5.1)]
- GI Bleeding, Ulceration and Perforation [see Warnings and Precautions (5.2)]
- Hepatotoxicity [see Warnings and Precautions (5.3)]
- Hypertension [see Warnings and Precautions (5.4)]
- Heart Failure and Edema [see Warnings and Precautions (5.5)]
- Renal Toxicity and Hyperkalemia [see Warnings and Precautions (5.6)]
- Anaphylactic Reactions [see Warnings and Precautions (5.7)]
- Serious Skin Reactions [see Warnings and Precautions (5.9)]
- Hematologic Toxicity [see Warnings and Precautions (5.12)]

6.1 Clinical Trials Experience

Because clinical trials are conducted under widely varying conditions, adverse reaction rates observed in the clinical trials of a drug cannot be directly compared to rates in the clinical trials of another drug and may not reflect the rates observed in practice. The adverse reaction information from clinical trials does, however, provide a basis for identifying the adverse events that appear to be related to drug use and for approximating rates.

Of the celecoxib-treated patients in the pre-marketing controlled clinical trials of another formulation of celecoxib, approximately 4,250 were patients with OA, approximately 2,100 were patients with RA, and approximately 1,050 were patients with post-surgical pain. More than 8,500 patients received a total daily dose of celecoxib of 200 mg (100 mg twice daily or 200 mg once daily) or more, including more than 400 treated at 800 mg (400 mg twice daily). Approximately 3,900 patients received celecoxib at these doses for 6 months or more; approximately 2,300 of these have received it for 1 year or more and 124 of these have received it for 2 years or more.

Pre-marketing Controlled Arthritis Trials

Table 1 lists all adverse events, regardless of causality, occurring in ≥2% of patients receiving celecoxib from 12 controlled studies conducted in patients with OA or RA that included a placebo and/or a positive control group. Since these 12 trials were of different durations, and patients in the trials may not have been exposed for the same duration of time, these percentages do not capture cumulative rates of occurrence.

Table 1: Adverse Events Occurring in >2% of Celecoxib Patients from Pre-marketing Controlled Arthritis Trials
 | CEL N=4146 | Placebo N=1864 | NAP N=1366 | DCF N=387 | IBU N=345
Gastrointestinal
Abdominal Pain | 4.1% | 2.8% | 7.7% | 9.0% | 9.0%
Diarrhea | 5.6% | 3.8% | 5.3% | 9.3% | 5.8%
Dyspepsia | 8.8% | 6.2% | 12.2% | 10.9% | 12.8%
Flatulence | 2.2% | 1.0% | 3.6% | 4.1% | 3.5%
Nausea | 3.5% | 4.2% | 6.0% | 3.4% | 6.7%
Body as a whole
Back Pain | 2.8% | 3.6% | 2.2% | 2.6% | 0.9%
Peripheral Edema | 2.1% | 1.1% | 2.1% | 1.0% | 3.5%
Injury-Accidental | 2.9% | 2.3% | 3.0% | 2.6% | 3.2%
Central, Peripheral Nervous system
Dizziness | 2.0% | 1.7% | 2.6% | 1.3% | 2.3%
Headache | 15.8% | 20.2% | 14.5% | 15.5% | 15.4%
Psychiatric
Insomnia | 2.3% | 2.3% | 2.9% | 1.3% | 1.4%
Respiratory
Pharyngitis | 2.3% | 1.1% | 1.7% | 1.6% | 2.6%
Rhinitis | 2.0% | 1.3% | 2.4% | 2.3% | 0.6%
Sinusitis | 5.0% | 4.3% | 4.0% | 5.4% | 5.8%
Upper Respiratory Infection | 8.1% | 6.7% | 9.9% | 9.8% | 9.9%
Skin
Rash | 2.2% | 2.1% | 2.1% | 1.3% | 1.2%
CEL = Celecoxib 100 mg to 200 mg twice daily or 200 mg once daily; NAP = Naproxen 500 mg twice daily;
DCF = Diclofenac 75 mg twice daily;
IBU = Ibuprofen 800 mg three times daily.

In placebo- or active-controlled clinical trials, the discontinuation rate due to adverse events was 7.1% for patients receiving celecoxib and 6.1% for patients receiving placebo. Among the most common reasons for discontinuation due to adverse events in the celecoxib treatment groups were dyspepsia and abdominal pain (cited as reasons for discontinuation in 0.8% and 0.7% of celecoxib patients, respectively).

Among patients receiving placebo, 0.6% discontinued due to dyspepsia and 0.6% withdrew due to abdominal pain.

The following adverse reactions occurred in 0.1% to 1.9% of patients treated with celecoxib (100 mg to 200 mg twice daily or 200 mg once daily):

Gastrointestinal: Constipation, diverticulitis, dysphagia, eructation, esophagitis, gastritis, gastroenteritis, gastroesophageal reflux, hemorrhoids, hiatal hernia, melena, dry mouth, stomatitis, tenesmus, vomiting

Cardiovascular: Aggravated hypertension, angina pectoris, coronary artery disorder, myocardial infarction

General: Hypersensitivity, allergic reaction, chest pain, cyst NOS, edema generalized, face edema, fatigue, fever, hot flushes, influenza-like symptoms, pain, peripheral pain

Central, peripheral nervous system: Leg cramps, hypertonia, hypoesthesia, migraine, paresthesia, vertigo

Hearing and vestibular: Deafness, tinnitus

Heart rate and rhythm: Palpitation, tachycardia

Liver and biliary: Hepatic enzyme increased (including SGOT increased, SGPT increased)

Metabolic and nutritional: blood urea nitrogen (BUN) increased, creatine phosphokinase (CPK) increased, hypercholesterolemia, hyperglycemia, hypokalemia, NPN increased, creatinine increased, alkaline phosphatase increased, weight increased

Musculoskeletal: Arthralgia, arthrosis, myalgia, synovitis, tendinitis

Platelets (bleeding or clotting): Ecchymosis, epistaxis, thrombocythemia,

Psychiatric: Anorexia, anxiety, appetite increased, depression, nervousness, somnolence

Hemic: Anemia

Respiratory: Bronchitis, bronchospasm, bronchospasm aggravated, cough, dyspnea, laryngitis, pneumonia

Skin and appendages: Alopecia, dermatitis, photosensitivity reaction, pruritus, rash erythematous, rash maculopapular, skin disorder, skin dry, sweating increased, urticaria

Application site disorders: Cellulitis, dermatitis contact

Urinary: Albuminuria, cystitis, dysuria, hematuria, micturition frequency, renal calculus

The following serious adverse events (causality not evaluated) occurred in <0.1% of patients:

Cardiovascular: Syncope, congestive heart failure, ventricular fibrillation, pulmonary embolism, cerebrovascular accident, peripheral gangrene, thrombophlebitis

Gastrointestinal: Intestinal obstruction, intestinal perforation, gastrointestinal bleeding, colitis with bleeding, esophageal perforation, pancreatitis, ileus

General: Sepsis, sudden death

Liver and biliary: Cholelithiasis

Hemic and lymphatic: Thrombocytopenia

Nervous: Ataxia, suicide [see Drug Interactions (7)]

Renal: Acute renal failure

The Celecoxib Long-Term Arthritis Safety Study [see Clinical Studies (14.6)]

Hematological Events: The incidence of clinically significant decreases in hemoglobin (>2 g/dL) was lower in patients on celecoxib 400 mg twice daily (0.5%) compared to patients on either diclofenac 75 mg twice daily (1.3%) or ibuprofen 800 mg three times daily 1.9%. The lower incidence of events with celecoxib was maintained with or without aspirin use [see Clinical Pharmacology (12.2)].

Withdrawals/Serious Adverse Events: Kaplan-Meier cumulative rates at 9 months for withdrawals due to adverse events for celecoxib, diclofenac and ibuprofen were 24%, 29%, and 26%, respectively. Rates for serious adverse events (i.e., causing hospitalization or felt to be life-threatening or otherwise medically significant), regardless of causality, were not different across treatment groups (8%, 7%, and 8%, respectively).

Juvenile Rheumatoid Arthritis Study

In a 12-week, double-blind, active-controlled study, 242 JRA patients 2 years to 17 years of age were treated with celecoxib or naproxen; 77 JRA patients were treated with celecoxib 3 mg/kg twice daily, 82 patients were treated with celecoxib 6 mg/kg twice daily, and 83 patients were treated with naproxen 7.5 mg/kg twice daily. The most commonly occurring (≥5%) adverse events in celecoxib treated patients were headache, fever (pyrexia), upper abdominal pain, cough, nasopharyngitis, abdominal pain, nausea, arthralgia, diarrhea, and vomiting. The most commonly occurring (≥5%) adverse experiences for naproxen-treated patients were headache, nausea, vomiting, fever, upper abdominal pain, diarrhea, cough, abdominal pain, and dizziness (Table 2). Compared with naproxen, celecoxib at doses of 3 and 6 mg/kg twice daily had no observable deleterious effect on growth and development during the course of the 12-week double-blind study. There was no substantial difference in the number of clinical exacerbations of uveitis or systemic features of JRA among treatment groups.

In a 12-week, open-label extension of the double-blind study described above, 202 JRA patients were treated with celecoxib 6 mg/kg twice daily. The incidence of adverse events was similar to that observed during the double-blind study; no unexpected adverse events of clinical importance emerged.

Table 2: Adverse Events Occurring in ≥5% of JRA Patients in Any Treatment Group, by System Organ Class (% of patients with events)
 | All Doses Twice Daily
System Organ Class Preferred Term | Celecoxib 3 mg/kg N=77 | Celecoxib 6 mg/kg N=82 | Naproxen 7.5 mg/kg N=83
Any Event | 64 | 70 | 72
Eye Disorders | 5 | 5 | 5
Gastrointestinal | 26 | 24 | 36
Abdominal pain NOS | 4 | 7 | 7
Abdominal pain upper | 8 | 6 | 10
Vomiting NOS | 3 | 6 | 11
Diarrhea NOS | 5 | 4 | 8
Nausea | 7 | 4 | 11
General | 13 | 11 | 18
Pyrexia | 8 | 9 | 11
Infections | 25 | 20 | 27
Nasopharyngitis | 5 | 6 | 5
Injury and Poisoning | 4 | 6 | 5
Investigations [Abnormal laboratory tests, which include: Prolonged activated partial thromboplastin time, Bacteriuria NOS present, Blood creatine phosphokinase increased, Blood culture positive, Blood glucose increased, Blood pressure increased, Blood uric acid increased, Hematocrit decreased, Hematuria present, Hemoglobin decreased, Liver function tests NOS abnormal, Proteinuria present, Transaminase NOS increased, Urine analysis abnormal NOS] | 3 | 11 | 7
Musculoskeletal | 8 | 10 | 17
Arthralgia | 3 | 7 | 4
Nervous System | 17 | 11 | 21
Headache NOS | 13 | 10 | 16
Dizziness (excl vertigo) | 1 | 1 | 7
Respiratory | 8 | 15 | 15
Cough | 7 | 7 | 8
Skin & Subcutaneous | 10 | 7 | 18

Other Pre-Approval Studies

Adverse Events from Ankylosing Spondylitis Studies: A total of 378 patients were treated with celecoxib in placebo- and active-controlled AS studies. Doses up to 400 mg once daily were studied. The types of adverse events reported in the AS studies were similar to those reported in the OA/RA studies.

Adverse Events from Analgesia and Dysmenorrhea Studies: Approximately 1,700 patients were treated with celecoxib in analgesia and dysmenorrhea studies. All patients in post-oral surgery pain studies received a single dose of study medication. Doses up to 600 mg/day of celecoxib were studied in primary dysmenorrhea and post-orthopedic surgery pain studies. The types of adverse events in the analgesia and dysmenorrhea studies were similar to those reported in arthritis studies. The only additional adverse event reported was post-dental extraction alveolar osteitis (dry socket) in the post-oral surgery pain studies.

The APC and PreSAP Trials

Adverse reactions from long-term, placebo-controlled polyp prevention studies: Exposure to celecoxib in the APC and PreSAP trials was 400 mg to 800 mg daily for up to 3 years [see Clinical Studies (14.6)].

Some adverse reactions occurred in higher percentages of patients than in the arthritis pre-marketing trials (treatment durations up to 12 weeks; see Adverse events from celecoxib pre-marketing controlled arthritis trials, above). The adverse reactions for which these differences in patients treated with celecoxib were greater as compared to the arthritis pre-marketing trials were as follows:

 | Celecoxib (400 to 800 mg daily) N = 2285 | Placebo N=1303
Diarrhea | 10.5% | 7.0%
Gastroesophageal reflux disease | 4.7% | 3.1%
Nausea | 6.8% | 5.3%
Vomiting | 3.2% | 2.1%
Dyspnea | 2.8% | 1.6%
Hypertension | 12.5% | 9.8%
Nephrolithiasis | 2.1% | 0.8%

The following additional adverse reactions occurred in ≥0.1% and <1% of patients taking celecoxib, at an incidence greater than placebo in the long-term polyp prevention studies, and were either not reported during the controlled arthritis pre-marketing trials or occurred with greater frequency in the long-term, placebo-controlled polyp prevention studies:

Nervous system disorders: Cerebral infarction

Eye disorders: Vitreous floaters, conjunctival hemorrhage

Ear and labyrinth: Labyrinthitis

Cardiac disorders: Angina unstable, aortic valve incompetence, coronary artery atherosclerosis, sinus bradycardia, ventricular hypertrophy

Vascular disorders: Deep vein thrombosis

Reproductive system and breast disorders: Ovarian cyst

Investigations: Blood potassium increased, blood sodium increased, blood testosterone decreased

Injury, poisoning, and procedural complications: Epicondylitis, tendon rupture

6.2 Postmarketing Experience

The following adverse reactions have been identified during post approval use of celecoxib. Because these reactions are reported voluntarily from a population of uncertain size, it is not always possible to reliably estimate their frequency or establish a causal relationship to drug exposure

Cardiovascular: Vasculitis, deep venous thrombosis

General: Anaphylactoid reaction, angioedema

Liver and biliary: Liver necrosis, hepatitis, jaundice, hepatic failure

Hemic and lymphatic: Agranulocytosis, aplastic anemia, pancytopenia, leucopenia

Metabolic: Hypoglycemia, hyponatremia

Nervous: Aseptic meningitis, ageusia, anosmia, fatal intracranial hemorrhage

Renal: Interstitial nephritis

Skin and Appendages: Erythema multiforme, exfoliative dermatitis, Stevens-Johnson Syndrome (SJS), toxic epidermal necrolysis (TEN), drug reaction with eosinophilia and systemic symptoms (DRESS), acute generalized exanthematous pustulosis (AGEP), and fixed drug eruption (FDE).

7. DRUG INTERACTIONS

See Table 3 for clinically significant drug interactions with celecoxib.

Table 3: Clinically Significant Drug Interactions with Celecoxib
Drugs That Interfere with Hemostasis
Clinical Impact: | - Celecoxib and anticoagulants such as warfarin have a synergistic effect on bleeding. The concomitant use of Celecoxib and anticoagulants have an increased risk of serious bleeding compared to the use of either drug alone. - Serotonin release by platelets plays an important role in hemostasis. Case-control and cohort epidemiological studies showed that concomitant use of drugs that interfere with serotonin reuptake and an NSAID may potentiate the risk of bleeding more than an NSAID alone.
Intervention: | Monitor patients with concomitant use of VYSCOXA with anticoagulants (e.g., warfarin), antiplatelet drugs (e.g., aspirin), SSRIs, and SNRIs for signs of bleeding [see Warnings and Precautions (5.12)].
Aspirin
Clinical Impact: | Controlled clinical studies showed that the concomitant use of NSAIDs and analgesic doses of aspirin does not produce any greater therapeutic effect than the use of NSAIDs alone. In a clinical study, the concomitant use of an NSAID and aspirin was associated with a significantly increased incidence of GI adverse reactions as compared to use of the NSAID alone [see Warnings and Precautions (5.2)]. In two studies in healthy volunteers, and in patients with osteoarthritis and established heart disease respectively, celecoxib (200 mg to 400 mg daily) has demonstrated a lack of interference with the cardioprotective antiplatelet effect of aspirin (100 mg to 325 mg).
Intervention: | Concomitant use of VYSCOXA and analgesic doses of aspirin is not generally recommended because of the increased risk of bleeding [see Warnings and Precautions (5.12)]. VYSCOXA is not a substitute for low dose aspirin for cardiovascular protection.
ACE Inhibitors, Angiotensin Receptor Blockers, and Beta-Blockers
Clinical Impact: | - NSAIDs may diminish the antihypertensive effect of ACE inhibitors, ARBs, or beta-blockers (including propranolol). - In patients who are elderly, volume-depleted (including those on diuretic therapy), or have renal impairment, co-administration of an NSAID with ACE inhibitors or ARBs may result in deterioration of renal function, including possible acute renal failure. These effects are usually reversible.
Intervention: | - During concomitant use of VYSCOXA and ACE inhibitors, ARBs, or beta-blockers, monitor blood pressure to ensure that the desired blood pressure is obtained. - During concomitant use of VYSCOXA and ACE inhibitors or ARBs in patients who are elderly, volume-depleted, or have impaired renal function, monitor for signs of worsening renal function [see Warnings and Precautions (5.6)]. - When these drugs are administered concomitantly, patients should be adequately hydrated. Assess renal function at the beginning of the concomitant treatment and periodically thereafter.
Diuretics
Clinical Impact: | Clinical studies, as well as post-marketing observations, showed that NSAIDs reduced the natriuretic effect of loop diuretics (e.g., furosemide) and thiazide diuretics in some patients. This effect has been attributed to the NSAID inhibition of renal prostaglandin synthesis.
Intervention: | During concomitant use of VYSCOXA with diuretics, observe patients for signs of worsening renal function, in addition to assuring diuretic efficacy including antihypertensive effects [see Warnings and Precautions (5.6)].
Digoxin
Clinical Impact: | The concomitant use of Celecoxib with digoxin has been reported to increase the serum concentration and prolong the half-life of digoxin.
Intervention: | During concomitant use of VYSCOXA and digoxin, monitor serum digoxin levels.
Lithium
Clinical Impact: | NSAIDs have produced elevations in plasma lithium levels and reductions in renal lithium clearance. The mean minimum lithium concentration increased 15%, and the renal clearance decreased by approximately 20%. This effect has been attributed to NSAID inhibition of renal prostaglandin synthesis.
Intervention: | During concomitant use of VYSCOXA and lithium, monitor patients for signs of lithium toxicity.
Methotrexate
Clinical Impact: | Concomitant use of NSAIDs and methotrexate may increase the risk for methotrexate toxicity (e.g., neutropenia, thrombocytopenia, renal dysfunction). Celecoxib has no effect on methotrexate pharmacokinetics.
Intervention: | During concomitant use of VYSCOXA and methotrexate, monitor patients for methotrexate toxicity.
Cyclosporine
Clinical Impact: | Concomitant use of celecoxib and cyclosporine may increase cyclosporine's nephrotoxicity.
Intervention: | During concomitant use of VYSCOXA and cyclosporine, monitor patients for signs of worsening renal function.
NSAIDs and Salicylates
Clinical Impact: | Concomitant use of Celecoxib with other NSAIDs or salicylates (e.g., diflunisal, salsalate) increases the risk of GI toxicity, with little or no increase in efficacy [see Warnings and Precautions (5.2)].
Intervention: | The concomitant use of Celecoxib with other NSAIDs or salicylates is not recommended.
Pemetrexed
Clinical Impact: | Concomitant use of celecoxib and pemetrexed may increase the risk of pemetrexed-associated myelosuppression, renal, and GI toxicity (see the pemetrexed prescribing information).
Intervention: | During concomitant use of VYSCOXA and pemetrexed, in patients with renal impairment whose creatinine clearance ranges from 45 to 79 mL/min, monitor for myelosuppression, renal and GI toxicity. NSAIDs with short elimination half-lives (e.g., diclofenac, indomethacin) should be avoided for a period of two days before, the day of, and two days following administration of pemetrexed. In the absence of data regarding potential interaction between pemetrexed and NSAIDs with longer half-lives (e.g., meloxicam, nabumetone), patients taking these NSAIDs should interrupt dosing for at least five days before, the day of, and two days following pemetrexed administration.
CYP2C9 Inhibitors or inducers
Clinical Impact: | Celecoxib metabolism is predominantly mediated via cytochrome P450 (CYP) 2C9 in the liver. Co-administration of celecoxib with drugs that are known to inhibit CYP2C9 (e.g., fluconazole) may enhance the exposure and toxicity of celecoxib whereas co-administration with CYP2C9 inducers (e.g., rifampin) may lead to compromised efficacy of celecoxib.
Intervention | Evaluate each patient's medical history when consideration is given to prescribing VYSCOXA. A dosage adjustment may be warranted when VYSCOXA is administered with CYP2C9 inhibitors or inducers [see Clinical Pharmacology (12.3)].
CYP2D6 substrates
Clinical Impact: | In vitro studies indicate that celecoxib, although not a substrate, is an inhibitor of CYP2D6. Therefore, there is a potential for an in vivo drug interaction with drugs that are metabolized by CYP2D6 (e.g., atomoxetine), and celecoxib may enhance the exposure and toxicity of these drugs.
Intervention | Evaluate each patient's medical history when consideration is given to prescribing VYSCOXA. A dosage adjustment may be warranted when VYSCOXA is administered with CYP2D6 substrates [see Clinical Pharmacology (12.3)].
Corticosteroids
Clinical Impact: | Concomitant use of corticosteroids with celecoxib may increase the risk of GI ulceration or bleeding.
Intervention | Monitor patients with concomitant use of VYSCOXA with corticosteroids for signs of bleeding [see Warnings and Precautions (5.2)].

8. USE IN SPECIFIC POPULATIONS

8.1 Pregnancy

Risk Summary

Use of NSAIDs, including VYSCOXA, can cause premature closure of the fetal ductus arteriosus and fetal renal dysfunction leading to oligohydramnios and, in some cases, neonatal renal impairment. Because of these risks, limit dose and duration of VYSCOXA use between about 20 and 30 weeks of gestation and avoid VYSCOXA use at about 30 weeks of gestation and later in pregnancy (see Clinical Considerations, Data).

Premature Closure of Fetal Ductus Arteriosus

Use of NSAIDs, including VYSCOXA, at about 30 weeks gestation or later in pregnancy increases the risk of premature closure of the fetal ductus arteriosus.

Oligohydramnios/Neonatal Renal Impairment

Use of NSAIDs at about 20 weeks gestation or later in pregnancy has been associated with cases of fetal renal dysfunction leading to oligohydramnios, and in some cases, neonatal renal impairment.

Data from observational studies regarding other potential embryofetal risks of NSAID use in women in the first or second trimesters of pregnancy are inconclusive. In animal reproduction studies, embryo-fetal deaths and an increase in diaphragmatic hernias were observed in rats administered celecoxib daily during the period of organogenesis at oral doses approximately 6 times the maximum recommended human dose (MRHD) of 200 mg twice daily. In addition, structural abnormalities (e.g., septal defects, ribs fused, sternebrae fused and sternebrae misshapen) were observed in rabbits given daily oral doses of celecoxib during the period of organogenesis at approximately 2 times the MRHD (see Data). Based on animal data, prostaglandins have been shown to have an important role in endometrial vascular permeability, blastocyst implantation, and decidualization. In animal studies, administration of prostaglandin synthesis inhibitors such as celecoxib, resulted in increased pre- and post-implantation loss. Prostaglandins also have been shown to have an important role in fetal kidney development. In published animal studies, prostaglandin synthesis inhibitors have been reported to impair kidney development when administered at clinically relevant doses.

The background risk of major birth defects and miscarriage for the indicated population is unknown. All pregnancies have a background risk of birth defect, loss, or other adverse outcomes. In the U.S. general population, the estimated background risk of major birth defects and miscarriage in clinically recognized pregnancies is 2% to 4% and 15% to 20%, respectively.

Clinical Considerations

Fetal/Neonatal Adverse Reactions

Premature Closure of Fetal Ductus Arteriosus:

Avoid use of NSAIDs in women at about 30 weeks gestation and later in pregnancy, because NSAIDs, including VYSCOXA, can cause premature closure of the fetal ductus arteriosus (see Data).

Oligohydramnios/Neonatal Renal Impairment:

If an NSAID is necessary at about 20 weeks gestation or later in pregnancy, limit the use to the lowest effective dose and shortest duration possible. If VYSCOXA treatment extends beyond 48 hours, consider monitoring with ultrasound for oligohydramnios. If oligohydramnios occurs, discontinue VYSCOXA and follow up according to clinical practice (see Data).

Labor or Delivery

There are no studies on the effects of celecoxib during labor or delivery. In animal studies, NSAIDs, including celecoxib, inhibit prostaglandin synthesis, cause delayed parturition, and increase the incidence of stillbirth.

Data

Human Data

The available data do not establish the presence or absence of developmental toxicity related to the use of celecoxib.

Premature Closure of Fetal Ductus Arteriosus:

Published literature reports that the use of NSAIDs at about 30 weeks of gestation and later in pregnancy may cause premature closure of the fetal ductus arteriosus.

Oligohydramnios/Neonatal Renal Impairment:

Published studies and postmarketing reports describe maternal NSAID use at about 20 weeks gestation or later in pregnancy associated with fetal renal dysfunction leading to oligohydramnios, and in some cases, neonatal renal impairment. These adverse outcomes are seen, on average, after days to weeks of treatment, although oligohydramnios has been infrequently reported as soon as 48 hours after NSAID initiation. In many cases, but not all, the decrease in amniotic fluid was transient and reversible with cessation of the drug. There have been a limited number of case reports of maternal NSAID use and neonatal renal dysfunction without oligohydramnios, some of which were irreversible. Some cases of neonatal renal dysfunction required treatment with invasive procedures, such as exchange transfusion or dialysis.

Methodological limitations of these postmarketing studies and reports include lack of a control group; limited information regarding dose, duration, and timing of drug exposure; and concomitant use of other medications. These limitations preclude establishing a reliable estimate of the risk of adverse fetal and neonatal outcomes with maternal NSAID use. Because the published safety data on neonatal outcomes involved mostly preterm infants, the generalizability of certain reported risks to the full-term infant exposed to NSAIDs through maternal use is uncertain.

Animal data

Celecoxib at oral doses ≥150 mg/kg/day (approximately 2 times the human exposure at 200 mg twice daily as measured by AUC0–24h), caused an increased incidence of ventricular septal defects, a rare event, and fetal alterations, such as ribs fused, sternebrae fused and sternebrae misshapen when rabbits were treated throughout organogenesis. A dose-dependent increase in diaphragmatic hernias was observed when rats were given celecoxib at oral doses ≥30 mg/kg/day (approximately 6 times human exposure based on the AUC0–24h at 200 mg twice daily for RA) throughout organogenesis. In rats, exposure to celecoxib during early embryonic development resulted in pre-implantation and post-implantation losses at oral doses ≥50 mg/kg/day (approximately 6 times human exposure based on the AUC0–24h at 200 mg twice daily for RA).

Celecoxib produced no evidence of delayed labor or parturition at oral doses up to 100 mg/kg in rats (approximately 7-fold human exposure as measured by the AUC0–24h at 200 mg twice daily). The effects of celecoxib on labor and delivery in pregnant women are unknown.

8.2 Lactation

Risk Summary

Limited data from 3 published reports that included a total of 12 breastfeeding women showed low levels of celecoxib in breast milk. The calculated average daily infant dose was 10 to 40 mcg/kg/day, less than 1% of the weight-based therapeutic dose for a two-year old-child. A report of two breastfed infants 17 and 22 months of age did not show any adverse events. Caution should be exercised when VYSCOXA is administered to a nursing woman. The developmental and health benefits of breastfeeding should be considered along with the mother's clinical need for VYSCOXA and any potential adverse effects on the breastfed infant from the VYSCOXA or from the underlying maternal condition.

8.3 Females and Males of Reproductive Potential

Infertility

Females

Based on the mechanism of action, the use of prostaglandin-mediated NSAIDs, including VYSCOXA, may delay or prevent rupture of ovarian follicles, which has been associated with reversible infertility in some women. Published animal studies have shown that administration of prostaglandin synthesis inhibitors has the potential to disrupt prostaglandin mediated follicular rupture required for ovulation. Small studies in women treated with NSAIDs have also shown a reversible delay in ovulation. Consider withdrawal of NSAIDs, including VYSCOXA, in women who have difficulties conceiving or who are undergoing investigation of infertility.

8.4 Pediatric Use

The safety and effectiveness of celecoxib for the management of the signs and symptoms of Juvenile Rheumatoid Arthritis have been established in pediatric patients 2 years of age and older. The use of celecoxib in patients 2 years of age and older is supported by evidence from a 12-week, double-blind, active-controlled, pharmacokinetic, safety and efficacy study, with a 12-week open-label extension conducted in patients 2 to 17 years of age. Safety and efficacy have not been studied beyond six months in pediatric patients.

Patients with systemic onset JRA (without active systemic features) appear to be at risk for the development of abnormal coagulation laboratory tests. In some patients with systemic onset JRA, both celecoxib and naproxen were associated with mild prolongation of activated partial thromboplastin time (APTT) but not prothrombin time (PT). When NSAIDs including celecoxib are used in patients with systemic onset JRA, monitor patients for signs and symptoms of abnormal clotting or bleeding, due to the risk of disseminated intravascular coagulation. Patients with systemic onset JRA should be monitored for the development of abnormal coagulation tests. The long-term cardiovascular toxicity in children exposed to celecoxib has not been evaluated and it is unknown if long-term risks may be similar to that seen in adults exposed to celecoxib or other COX-2 selective and non- selective NSAIDs [see Boxed Warning, Dosage and Administration (2.3), Warnings and Precautions (5.15), Warnings and Precautions (5.5), Adverse Reactions (6.1), Animal Toxicology (13.2), Clinical Studies (14.4)].

Alternative therapies for treatment of JRA should be considered in pediatric patients identified to be CYP2C9 poor metabolizers [see Poor Metabolizers of CYP2C9 substrates (8.8)].

The safety and effectiveness of VYSCOXA have not been established in pediatric patients with JRA less than 2 years of age, in patients with a body weight less than 10 kg, and in patients with active systemic features.

The safety and effectiveness of VYSCOXA have not been established in pediatric patients for osteoarthritis or ankylosing spondylitis.

8.5 Geriatric Use

Elderly patients, compared to younger patients, are at greater risk for NSAID-associated serious cardiovascular, gastrointestinal, and/or renal adverse reactions. If the anticipated benefit for the elderly patient outweighs these potential risks, start dosing at the low end of the dosing range, and monitor patients for adverse effects [see Warnings and Precautions (5.1, 5.2, 5.3, 5.6, 5.14)].

Of the total number of patients who received celecoxib in pre-approval clinical trials, more than 3,300 were 65–74 years of age, while approximately 1,300 additional patients were 75 years and over. No substantial differences in effectiveness were observed between these subjects and younger subjects. In clinical studies comparing renal function as measured by the GFR, BUN and creatinine, and platelet function as measured by bleeding time and platelet aggregation, the results were not different between elderly and young volunteers. However, as with other NSAIDs, including those that selectively inhibit COX-2, there have been more spontaneous post-marketing reports of fatal GI events and acute renal failure in the elderly than in younger patients [see Warnings and Precautions (5.2, 5.6)].

8.6 Hepatic Impairment

The daily recommended dose of VYSCOXA oral suspension in patients with moderate hepatic impairment (Child-Pugh Class B) should be reduced by 50%. The use of VYSCOXA in patients with severe hepatic impairment is not recommended [see Dosage and Administration (2.6) and Clinical Pharmacology (12.3)].

8.7 Renal Impairment

VYSCOXA is not recommended in patients with severe renal insufficiency [see Warnings and Precautions (5.6) and Clinical Pharmacology (12.3)].

8.8 Poor Metabolizers of CYP2C9 Substrates

In patients who are known or suspected to be poor CYP2C9 metabolizers (i.e., CYP2C9*3/*3), based on genotype or previous history/experience with other CYP2C9 substrates (such as warfarin, phenytoin) administer VYSCOXA starting with half the lowest recommended dose. Alternative management should be considered in JRA patients identified to be CYP2C9 poor metabolizers [see Dosage and Administration (2.6) and Clinical Pharmacology (12.5)].

10. OVERDOSAGE

Symptoms following acute NSAID overdosages have been typically limited to lethargy, drowsiness, nausea, vomiting, and epigastric pain, which have been generally reversible with supportive care. Gastrointestinal bleeding has occurred. Hypertension, acute renal failure, respiratory depression, and coma have occurred, but were rare [see Warnings and Precautions (5.2, 5.4, 5.6)].

No overdoses of celecoxib were reported during clinical trials. Doses up to 2400 mg/day for up to 10 days in 12 patients did not result in serious toxicity. No information is available regarding the removal of celecoxib by hemodialysis, but based on its high degree of plasma protein binding (>97%) dialysis is unlikely to be useful in overdose.

Manage patients with symptomatic and supportive care following an NSAID overdosage. There are no specific antidotes. Consider emesis and/or activated charcoal (60 to 100 grams in adults, 1 to 2 grams per kg of body weight in pediatric patients) and/or osmotic cathartic in symptomatic patients seen within four hours of ingestion or in patients with a large overdosage (5 to 10 times the recommended dosage). Forced diuresis, alkalinization of urine, hemodialysis, or hemoperfusion may not be useful due to high protein binding.

For additional information about overdosage treatment contact a poison control center (1-800-222-1222).

11. DESCRIPTION

VYSCOXA contains celecoxib, a nonsteroidal anti-inflammatory agent. The chemical name of celecoxib is 4-[5-(4-methylphenyl)- 3-(trifluoromethyl)-1H-pyrazol-1-yl] benzenesulfonamide. Celecoxib has a molecular weight of is 381.38 g/mol, a molecular formula of C17H14F3N3O2S, and the following structural formula:

Celecoxib is a white to off-white powder with a pKa of 11.1 (sulfonamide moiety). Celecoxib is hydrophobic (log P is 3.5) and is practically insoluble in aqueous media at physiological pH range.

The inactive ingredients in VYSCOXA oral suspension include: anhydrous citric acid, glycerin, magnesium aluminometasilicate, methylparaben, propylparaben, purified water, sodium citrate dihydrate, sucralose, and xanthan gum. Sodium hydroxide and hydrochloric acid may be used to adjust the pH to 4.5 – 5.5.

12. CLINICAL PHARMACOLOGY

12.1 Mechanism of Action

Celecoxib has analgesic, anti-inflammatory, and antipyretic properties.

The mechanism of action of celecoxib is believed to be due to inhibition of prostaglandin synthesis, primarily via inhibition of COX-2. Celecoxib is a potent inhibitor of prostaglandin synthesis in vitro. Celecoxib concentrations reached during therapy have produced in vivo effects. Prostaglandins sensitize afferent nerves and potentiate the action of bradykinin in inducing pain in animal models. Prostaglandins are mediators of inflammation. Since celecoxib is an inhibitor of prostaglandin synthesis, its mode of action may be due to a decrease of prostaglandins in peripheral tissues.

12.2 Pharmacodynamics

Platelets

In clinical trials using normal volunteers, another formulation of celecoxib at single doses up to 800 mg and multiple doses of 600 mg twice daily for up to 7 days duration (higher than recommended therapeutic doses) had no effect on reduction of platelet aggregation or increase in bleeding time.

Because of its lack of platelet effects, celecoxib is not a substitute for aspirin for cardiovascular prophylaxis. It is not known if there are any effects of celecoxib on platelets that may contribute to the increased risk of serious cardiovascular thrombotic adverse events associated with the use of celecoxib.

Fluid Retention

Inhibition of PGE2 synthesis may lead to sodium and water retention through increased reabsorption in the renal medullary thick ascending loop of Henle and perhaps other segments of the distal nephron. In the collecting ducts, PGE2 appears to inhibit water reabsorption by counteracting the action of antidiuretic hormone.

12.3 Pharmacokinetics

Celecoxib has extensive distribution and high protein binding. It is primarily metabolized by CYP2C9 with a half-life of approximately 11 hours.

Absorption

Following a single dose administration of 200 mg VYSCOXA and 200 mg celecoxib capsules under fasting condition in 52 healthy subjects, the median time to peak plasma levels (i.e.,Tmax) of celecoxib was 1.5 hours (range 0.67 – 8.00 hours) and 2.5 hours (range 1.00 – 8.00 hours), respectively. The overall systemic exposure (AUC) of a 200 mg dose of VYSCOXA was equivalent to celecoxib capsules with a decrease in peak plasma levels (i.e., Cmax) of 22%. There were no significant alterations in terminal half-life values between VYSCOXA and celecoxib capsules. When celecoxib capsules were administered under fasting condition, both Cmax and AUC were roughly dose-proportional up to 200 mg twice daily, at higher dose there were less than proportional increases in Cmax and AUC which is thought to be due to the low solubility of the drug in aqueous media. The comparative bioavailability between VYSCOXA and celecoxib capsules at doses above 200 mg has not been determined. Absolute bioavailability studies have not been conducted. With multiple dosing of celecoxib, steady-state conditions are reached on or before Day 5.

Effects of Food

When a single dose of 200 mg VYSCOXA was taken with a high fat, high-calorie meal, the median Tmax was delayed by 1.5 hours. The extent and rate of absorption of celecoxib was significantly increased when a single dose of 200 mg VYSCOXA was administered under fed conditions compared to the fasting state and showed an increase in the mean AUC(0-t), AUC(0-∞), and, Cmax of celecoxib by 50%, 35%, and 144%, respectively. [see Dosage and Administration (2.1)].

Distribution

In healthy subjects, celecoxib is highly protein bound (~97%) within the clinical dose range. In vitro studies indicate that celecoxib binds primarily to albumin and, to a lesser extent, α1-acid glycoprotein. The apparent volume of distribution at steady state (Vss/F) is approximately 400 L, suggesting extensive distribution into the tissues. Celecoxib is not preferentially bound to red blood cells.

Elimination

Metabolism

Celecoxib metabolism is primarily mediated via CYP2C9. Three metabolites, a primary alcohol, the corresponding carboxylic acid and its glucuronide conjugate, have been identified in human plasma. These metabolites are inactive as COX-1 or COX-2 inhibitors.

Excretion

Celecoxib is eliminated predominantly by hepatic metabolism with little (<3%) unchanged drug recovered in the urine and feces. Following a single oral dose of radiolabeled drug, approximately 57% of the dose was excreted in the feces and 27% was excreted into the urine. The primary metabolite in both urine and feces was the carboxylic acid metabolite (73% of dose) with low amounts of the glucuronide also appearing in the urine. It appears that the low solubility of the drug prolongs the absorption process making terminal half-life (t1/2) determinations more variable. The effective half-life is approximately 11 hours under fasted conditions. The apparent plasma clearance (CL/F) is about 500 mL/min.

Specific Populations

Geriatric

At steady state, elderly subjects (over 65 years old) had a 40% higher Cmax and a 50% higher AUC compared to the young subjects. In elderly females, celecoxib Cmax and AUC are higher than those for elderly males, but these increases are predominantly due to lower body weight in elderly females. Dose adjustment in the elderly is not generally necessary. However, for patients of less than 50 kg in body weight, initiate therapy at the lowest recommended dose [see Use in Specific Populations (8.5)].

Pediatric

The steady state pharmacokinetics of celecoxib administered as an investigational oral suspension was evaluated in 152 JRA patients 2 years to 17 years of age weighing ≥10 kg with pauciarticular or polyarticular course JRA and in patients with systemic onset JRA.

Population pharmacokinetic analysis indicated that the oral clearance (unadjusted for body weight) of celecoxib increases less than proportionally to increasing weight, with 10 kg and 25 kg patients predicted to have 40% and 24% lower clearance, respectively, compared with a 70 kg adult RA patient.

Twice-daily administration of 50 mg celecoxib to JRA patients weighing ≥12 to ≤25 kg and 100 mg celecoxib to JRA patients weighing >25 kg should achieve plasma concentrations similar to those observed in a clinical trial that demonstrated the non-inferiority of celecoxib to naproxen 7.5 mg/kg twice daily [see Dosage and Administration (2.4)]. Celecoxib has not been studied in JRA patients under the age of 2 years, in patients with body weight less than 10 kg (22 lbs), or beyond 24 weeks.

Race

Meta-analysis of pharmacokinetic studies has suggested an approximately 40% higher AUC of celecoxib in Blacks compared to Caucasians. The cause and clinical significance of this finding is unknown.

Hepatic Impairment

A pharmacokinetic study in subjects with mild (Child-Pugh Class A) and moderate (Child-Pugh Class B) hepatic impairment has shown that steady-state celecoxib AUC is increased about 40% and 180%, respectively, above that seen in healthy control subjects. Therefore, the daily recommended dose of VYSCOXA should be reduced by approximately 50% in patients with moderate (Child-Pugh Class B) hepatic impairment. Patients with severe hepatic impairment (Child-Pugh Class C) have not been studied. The use of VYSCOXA in patients with severe hepatic impairment is not recommended [see Dosage and Administration (2.6) and Use in Specific Populations (8.6)].

Renal Impairment

In a cross-study comparison, celecoxib AUC was approximately 40% lower in patients with chronic renal insufficiency (GFR 35–60 mL/min) than that seen in subjects with normal renal function. No significant relationship was found between GFR and celecoxib clearance. Patients with severe renal insufficiency have not been studied. Similar to other NSAIDs, VYSCOXA is not recommended in patients with severe renal insufficiency [see Warnings and Precautions (5.6)].

Drug Interaction Studies

In vitro studies indicate that celecoxib is not an inhibitor of cytochrome P450 2C9, 2C19 or 3A4.

In vivo studies have shown the following:

Aspirin

When NSAIDs were administered with aspirin, the protein binding of NSAIDs were reduced, although the clearance of free NSAID was not altered. The clinical significance of this interaction is not known. See Table 3 for clinically significant drug interactions of NSAIDs with aspirin [see Drug Interactions (7)].

Lithium

In a study conducted in healthy subjects, mean steady-state lithium plasma levels increased approximately 17% in subjects receiving lithium 450 mg twice daily with celecoxib 200 mg twice daily as compared to subjects receiving lithium alone [see Drug Interactions (7)].

Fluconazole

Concomitant administration of fluconazole at 200 mg once daily resulted in a two-fold increase in celecoxib plasma concentration. This increase is due to the inhibition of celecoxib metabolism via P450 2C9 by fluconazole [see Drug Interactions (7)].

Aluminum- and Magnesium Containing Antacids

Coadministration of celecoxib with an aluminum- and magnesium-containing antacids resulted in reduction in plasma celecoxib concentrations with a decrease of 37% in Cmax and 10% in AUC.

Other Drugs

The effects of celecoxib on the pharmacokinetics and/or pharmacodynamics of glyburide, ketoconazole, [see Drug Interactions (7)], phenytoin, and tolbutamide have been studied in vivo and clinically important interactions have not been found.

12.5 Pharmacogenomics

CYP2C9 activity is reduced in individuals with genetic polymorphisms that lead to reduced enzyme activity, such as those homozygous for the CYP2C9*2 and CYP2C9*3 polymorphisms. Limited data from 4 published reports that included a total of 8 subjects with the homozygous CYP2C9*3/*3 genotype showed celecoxib systemic levels that were 3- to 7-fold higher in these subjects compared to subjects with CYP2C9*1/*1 or *I/*3 genotypes. The pharmacokinetics of celecoxib have not been evaluated in subjects with other CYP2C9 polymorphisms, such as *2, *5, *6, *9 and *11. It is estimated that the frequency of the homozygous *3/*3 genotype is 0.3% to 1.0% in various ethnic groups [see Dosage and Administration (2.6), Use in Specific Populations (8.8)].

13. NONCLINICAL TOXICOLOGY

13.1 Carcinogenesis, Mutagenesis, Impairment of Fertility

Carcinogenesis

Celecoxib was not carcinogenic in Sprague-Dawley rats given oral doses up to 200 mg/kg for males and 10 mg/kg for females (approximately 2-to 4-times the human exposure as measured by the AUC0–24h at 200 mg twice daily) or in mice given oral doses up to 25 mg/kg for males and 50 mg/kg for females (approximately equal to human exposure as measured by the AUC0–24h at 200 mg twice daily) for two years.

Mutagenesis

Celecoxib was not mutagenic in an Ames test and a mutation assay in Chinese hamster ovary (CHO) cells, nor clastogenic in a chromosome aberration assay in CHO cells and an in vivo micronucleus test in rat bone marrow.

Impairment of Fertility

Celecoxib had no effect on male or female fertility or male reproductive function in rats at oral doses up to 600 mg/kg/day (approximately 11-times human exposure at 200 mg twice daily based on the AUC0–24h). At ≥50 mg/kg/day (approximately 6-times human exposure based on the AUC0–24h at 200 mg twice daily) there was increased preimplantation loss.

13.2 Animal Toxicology

An increase in the incidence of background findings of spermatocele with or without secondary changes such as epididymal hypospermia as well as minimal to slight dilation of the seminiferous tubules was seen in the juvenile rat. These reproductive findings while apparently treatment-related did not increase in incidence or severity with dose and may indicate an exacerbation of a spontaneous condition. Similar reproductive findings were not observed in studies of juvenile or adult dogs or in adult rats treated with celecoxib. The clinical significance of this observation is unknown.

14. CLINICAL STUDIES

The effectiveness of VYSCOXA has been established based on adequate and well-controlled studies of another formulation of celecoxib [see Clinical Pharmacology (12.3)]. Below is a display of the efficacy results of the adequate and well-controlled studies of celecoxib.

14.1 Osteoarthritis

Celecoxib has demonstrated significant reduction in joint pain compared to placebo. Celecoxib was evaluated for treatment of the signs and the symptoms of OA of the knee and hip in placebo- and active-controlled clinical trials of up to 12 weeks duration. In patients with OA, treatment with celecoxib 100 mg twice daily or 200 mg once daily resulted in improvement in WOMAC (Western Ontario and McMaster Universities) osteoarthritis index, a composite of pain, stiffness, and functional measures in OA. In three 12-week studies of pain accompanying OA flare, celecoxib doses of 100 mg twice daily and 200 mg twice daily provided significant reduction of pain within 24 to 48 hours of initiation of dosing. At doses of 100 mg twice daily or 200 mg twice daily the effectiveness of celecoxib was shown to be similar to that of naproxen 500 mg twice daily. Doses of 200 mg twice daily provided no additional benefit above that seen with 100 mg twice daily. A total daily dose of 200 mg has been shown to be equally effective whether administered as 100 mg twice daily or 200 mg once daily.

14.2 Rheumatoid Arthritis

Celecoxib has demonstrated significant reduction in joint tenderness/pain and joint swelling compared to placebo. Celecoxib was evaluated for treatment of the signs and symptoms of RA in placebo- and active-controlled clinical trials of up to 24 weeks in duration. Celecoxib was shown to be superior to placebo in these studies, using the ACR20 Responder Index, a composite of clinical, laboratory, and functional measures in RA. Celecoxib doses of 100 mg twice daily and 200 mg twice daily were similar in effectiveness and both were comparable to naproxen 500 mg twice daily.

Although celecoxib 100 mg twice daily and 200 mg twice daily provided similar overall effectiveness, some patients derived additional benefit from the 200 mg twice daily dose. Doses of 400 mg twice daily provided no additional benefit above that seen with 100 mg to 200 mg twice daily.

14.3 Ankylosing Spondylitis

Celecoxib was evaluated in AS patients in two placebo- and active-controlled clinical trials of 6 and 12 weeks duration. Celecoxib at doses of 100 mg twice daily, 200 mg once daily and 400 mg once daily was shown to be statistically superior to placebo in these studies for all three co-primary efficacy measures assessing global pain intensity (Visual Analogue Scale), global disease activity (Visual Analogue Scale) and functional impairment (Bath Ankylosing Spondylitis Functional Index). In the 12-week study, there was no difference in the extent of improvement between the 200 mg and 400 mg celecoxib doses in a comparison of mean change from baseline, but there was a greater percentage of patients who responded to celecoxib 400 mg, 53%, than to celecoxib 200 mg, 44%, using the Assessment in Ankylosing Spondylitis response criteria (ASAS 20). The ASAS 20 defines a responder as improvement from baseline of at least 20% and an absolute improvement of at least 10 mm, on a 0 mm to 100 mm scale, in at least three of the four following domains: patient global pain, Bath Ankylosing Spondylitis Functional Index, and inflammation. The responder analysis also demonstrated no change in the responder rates beyond 6 weeks.

14.4 Juvenile Rheumatoid Arthritis (NCT00652925)

In a 12-week, randomized, double-blind active-controlled, parallel-group, multicenter, noninferiority study, patients from 2 years to 17 years of age with pauciarticular, polyarticular course JRA or systemic onset JRA (with currently inactive systemic features), received one of the following treatments: celecoxib 3 mg/kg (to a maximum of 150 mg) twice daily; celecoxib 6 mg/kg (to a maximum of 300 mg) twice daily; or naproxen 7.5 mg/kg (to a maximum of 500 mg) twice daily. The response rates were based upon the JRA Definition of Improvement greater than or equal to 30% (JRA DOI 30) criterion, which is a composite of clinical, laboratory, and functional measures of JRA. The JRA DOI 30 response rates at week 12 were 69%, 80% and 67% in the celecoxib 3 mg/kg twice daily, celecoxib 6 mg/kg twice daily, and naproxen 7.5 mg/kg twice daily treatment groups, respectively.

The efficacy and safety of celecoxib for JRA have not been studied beyond six months. The long-term cardiovascular toxicity in children exposed to celecoxib has not been evaluated and it is unknown if the long-term risk may be similar to that seen in adults exposed to celecoxib or other COX-2 selective and non-selective NSAIDs [see Boxed Warning, Warnings and Precautions (5.1, 5.15)].

14.5 Cardiovascular Outcomes Trial: Prospective Randomized Evaluation of Celecoxib Integrated Safety vs. Ibuprofen Or Naproxen (PRECISION; NCT00346216)

Design

The PRECISION trial was a double-blind randomized controlled trial of cardiovascular safety in OA and RA patients with or at high risk for cardiovascular disease comparing celecoxib with naproxen and ibuprofen. Patients were randomized to a starting dose of 100 mg twice daily of celecoxib, 600 mg three times daily of ibuprofen, or 375 mg twice daily of naproxen, with the option of escalating the dose as needed for pain management. Based on labeled doses, OA patients randomized to celecoxib could not dose escalate.

The primary endpoint, the Antiplatelet Trialists' Collaboration (APTC) composite, was an independently adjudicated composite of cardiovascular death (including hemorrhagic death), non-fatal myocardial infarction, and non-fatal stroke with 80% power to evaluate non-inferiority. All patients were prescribed open-label esomeprazole (20–40 mg) for gastroprotection. Treatment randomization was stratified by baseline low-dose aspirin use.

Additionally, there was a 4-month substudy assessing the effects of the three drugs on blood pressure as measured by ambulatory monitoring.

Results

Among subjects with OA, only 0.2% (17/7259) escalated celecoxib to the 200 mg twice daily dose, whereas 54.7% (3946/7208) escalated ibuprofen to 800 mg three times daily, and 54.8% (3937/7178) escalated naproxen to the 500 mg twice daily dose. Among subjects with RA, 55.7% (453/813) escalated celecoxib to the 200 mg twice daily dose, 56.5% (470/832) escalated ibuprofen to 800 mg three times daily, and 54.6% (432/791) escalated naproxen to the 500 mg twice daily dose; however, the RA population accounted for only 10% of the trial population.

Because relatively few celecoxib patients overall (5.8% [470/8072]) dose-escalated to 200 mg twice daily, the results of the PRECISION trial are not suitable for determining the relative CV safety of celecoxib at 200 mg twice daily compared to ibuprofen and naproxen at the doses taken.

Primary Endpoint

The trial had two prespecified analysis populations:

- Intent-to-treat population (ITT): Comprised of all randomized subjects followed for a maximum of 30 months
- Modified Intent-to-treat population (mITT): Comprised of all randomized subjects who received at least one dose of study medication and had at least one post-baseline visit followed until the earlier of treatment discontinuation plus 30 days, or 43 months

Celecoxib, at the 100 mg twice daily dose, as compared with either naproxen or ibuprofen at the doses taken, met all four prespecified non-inferiority criteria (p<0.001 for non-inferiority in both comparisons) for the APTC endpoint, a composite of cardiovascular death (including hemorrhagic death), non-fatal myocardial infarction, and non-fatal stroke [see Table 5]. Non-inferiority was prespecified as a hazard ratio (HR) of ≤1.12 in both ITT and mITT analyses, and upper 95% CI of ≤1.33 for ITT analysis and ≤1.40 for mITT analysis.

The primary analysis results for ITT and mITT are described in Table 5.

Table 4. Primary Analysis of the Adjudicated APTC Composite Endpoint
Intent-To-Treat Analysis (ITT, through month 30)
 | Celecoxib | Ibuprofen | Naproxen
N | 8,072 | 8,040 | 7,969
Subjects with Events | 188 (2.3%) | 218 (2.7%) | 201 (2.5%)
Pairwise Comparison | Celecoxib vs. Naproxen | Celecoxib vs. Ibuprofen | Ibuprofen vs. Naproxen
HR (95% CI) | 0.93 (0.76, 1.13) | 0.86 (0.70, 1.04) | 1.08 (0.89, 1.31)
Modified Intent-To-Treat Analysis (mITT, on treatment plus 30 days, through month 43)
 | Celecoxib | Ibuprofen | Naproxen
N | 8,030 | 7,990 | 7,933
Subjects with Events | 134 (1.7%) | 155 (1.9%) | 144 (1.8%)
Pairwise Comparison | Celecoxib vs. Naproxen | Celecoxib vs. Ibuprofen | Ibuprofen vs. Naproxen
HR (95% CI) | 0.90 (0.72, 1.14) | 0.81 (0.64, 1.02) | 1.12 (0.89, 1.40)

Table 5. Summary of the Adjudicated APTC Components [A patient may have experienced more than one component; therefore, the sum of the components is larger than the number of patients who experienced the composite outcome]
Intent-To-Treat Analysis (ITT, through month 30)
 | Celecoxib | Ibuprofen | Naproxen
N | 8,072 | 8,040 | 7,969
CV Death | 68 (0.8%) | 80 (1.0%) | 86 (1.1%)
Non-Fatal MI | 76 (0.9%) | 92 (1.1%) | 66 (0.8%)
Non-Fatal Stroke | 51 (0.6%) | 53 (0.7%) | 57 (0.7%)
Modified Intent-To-Treat Analysis (mITT, on treatment plus 30 days, through month 43)
N | 8,030 | 7,990 | 7,933
CV Death | 35 (0.4%) | 51 (0.6%) | 49 (0.6%)
Non-fatal MI | 58 (0.7%) | 76 (1.0%) | 53 (0.7%)
Non-fatal Stroke | 43 (0.5%) | 32 (0.4%) | 45 (0.6%)

In the ITT analysis population through 30 months, all-cause mortality was 1.6% in the celecoxib group, 1.8% in the ibuprofen group, and 2.0% in the naproxen group.

Ambulatory Blood Pressure Monitoring (ABPM) Substudy

In the PRECISION-ABPM substudy, among the total of 444 analyzable patients at Month 4, celecoxib dosed at 100 mg twice daily decreased mean 24-hour systolic blood pressure (SBP) by 0.3 mmHg, whereas ibuprofen and naproxen at the doses taken increased mean 24-hour SBP by 3.7 and 1.6 mmHg, respectively. These changes resulted in a statistically significant and clinically meaningful difference of 3.9 mmHg (p=0.0009) between celecoxib and ibuprofen and a non-statistically significant difference of 1.8 (p=0.119) mmHg between celecoxib and naproxen.

14.6 Special Studies

Adenomatous Polyp Prevention Studies (NCT00005094 and NCT00141193)

Cardiovascular safety was evaluated in two randomized, double-blind, placebo-controlled, three-year studies involving patients with Sporadic Adenomatous Polyps treated with celecoxib: the APC trial (Adenoma Prevention with Celecoxib) and the PreSAP trial (Prevention of Spontaneous Adenomatous Polyps). In the APC trial, there was a dose-related increase in the composite endpoint (adjudicated) of cardiovascular death, myocardial infarction, or stroke with celecoxib compared to placebo over 3 years of treatment. The PreSAP trial did not demonstrate a statistically significant increased risk for the same composite endpoint (adjudicated):

- In the APC trial, the hazard ratios compared to placebo for a composite endpoint (adjudicated) of cardiovascular death, myocardial infarction, or stroke were 3.4 (95% CI 1.4 – 8.5) with celecoxib 400 mg twice daily and 2.8 (95% CI 1.1 – 7.2) with celecoxib 200 mg twice daily. Cumulative rates for this composite endpoint over 3 years were 3.0% (20/671 subjects) and 2.5% (17/685 subjects), respectively, compared to 0.9% (6/679 subjects) with placebo treatment. The increases in both celecoxib dose groups versus placebo-treated patients were mainly due to an increased incidence of myocardial infarction.
- In the PreSAP trial, the hazard ratio for this same composite endpoint (adjudicated) was 1.2 (95% CI 0.6 – 2.4) with celecoxib 400 mg once daily compared to placebo. Cumulative rates for this composite endpoint over 3 years were 2.3% (21/933 subjects) and 1.9% (12/628 subjects), respectively.

Clinical trials of other COX-2 selective and non-selective NSAIDs of up to three-years duration have shown an increased risk of serious cardiovascular thrombotic events, myocardial infarction, and stroke, which can be fatal. As a result, all NSAIDs are considered potentially associated with this risk.

Celecoxib Long-Term Arthritis Safety Study (CLASS)

This was a prospective, long-term, safety outcome study conducted post-marketing in approximately 5,800 OA patients and 2,200 RA patients. Patients received celecoxib 400 mg twice daily (4-fold and 2-fold the recommended OA and RA doses, respectively), ibuprofen 800 mg three times daily or diclofenac 75 mg twice daily (common therapeutic doses). Median exposures for celecoxib (n = 3,987) and diclofenac (n = 1,996) were 9 months while ibuprofen (n = 1,985) was 6 months. The primary endpoint of this outcome study was the incidence of complicated ulcers (gastrointestinal bleeding, perforation, or obstruction). Patients were allowed to take concomitant low-dose (≤ 325 mg/day) aspirin (ASA) for cardiovascular prophylaxis (ASA subgroups: celecoxib, n = 882; diclofenac, n = 445; ibuprofen, n = 412). Differences in the incidence of complicated ulcers between celecoxib and the combined group of ibuprofen and diclofenac were not statistically significant.

Patients on celecoxib and concomitant low-dose ASA (N=882) experienced 4-fold higher rates of complicated ulcers compared to those not on ASA (N=3105). The Kaplan-Meier rate for complicated ulcers at 9 months was 1.12% versus 0.32% for those on low-dose ASA and those not on ASA, respectively [see Warnings and Precautions (5.4)].

The estimated cumulative rates at 9 months of complicated and symptomatic ulcers for patients treated with celecoxib 400 mg twice daily are described in Table 6. Table 6 also displays results for patients less than or greater than 65 years of age. The difference in rates between celecoxib alone and celecoxib with ASA groups may be due to the higher risk for GI events in ASA users.

Table 6: Complicated and Symptomatic Ulcer Rates in Patients Taking Celecoxib 400 mg Twice Daily (Kaplan-Meier Rates at 9 months [%]) Based on Risk Factors
All Patients
Celecoxib alone (n=3105) | 0.78
Celecoxib with ASA (n=882) | 2.19
Patients <65 Years
Celecoxib alone (n=2025) | 0.47
Celecoxib with ASA (n=403) | 1.26
Patients ≥65 Years
Celecoxib alone (n=1080) | 1.40
Celecoxib with ASA (n=479) | 3.06

In a small number of patients with a history of ulcer disease, the complicated and symptomatic ulcer rates in patients taking celecoxib alone or celecoxib with ASA were, respectively, 2.56% (n=243) and 6.85% (n=91) at 48 weeks. These results are to be expected in patients with a prior history of ulcer disease [see Warnings and Precautions (5.2) and Adverse Reactions (6.1)].

Cardiovascular safety outcomes were also evaluated in the CLASS trial. Kaplan-Meier cumulative rates for investigator-reported serious cardiovascular thromboembolic adverse events (including MI, pulmonary embolism, deep venous thrombosis, unstable angina, transient ischemic attacks, and ischemic cerebrovascular accidents) demonstrated no differences between the celecoxib, diclofenac, or ibuprofen treatment groups. The cumulative rates in all patients at nine months for celecoxib, diclofenac, and ibuprofen were 1.2%, 1.4%, and 1.1%, respectively. The cumulative rates in non-ASA users at nine months in each of the three treatment groups were less than 1%. The cumulative rates for myocardial infarction in non-ASA users at nine months in each of the three treatment groups were less than 0.2%. There was no placebo group in the CLASS trial, which limits the ability to determine whether the three drugs tested had no increased risk of CV events or if they all increased the risk to a similar degree. In the CLASS study, the Kaplan-Meier cumulative rates at 9 months of peripheral edema in patients on celecoxib 400 mg twice daily (4-fold and 2-fold the recommended OA and RA doses, respectively), ibuprofen 800 mg three times daily and diclofenac 75 mg twice daily were 4.5%, 6.9% and 4.7%, respectively. The rates of hypertension from the CLASS trial in the celecoxib, ibuprofen and diclofenac-treated patients were 2.4%, 4.2% and 2.5%, respectively.

Endoscopic Studies

The correlation between findings of short-term endoscopic studies with celecoxib and the relative incidence of clinically significant serious upper GI events with long-term use has not been established. Serious clinically significant upper GI bleeding has been observed in patients receiving celecoxib in controlled and open-labeled trials [see Warnings and Precautions (5.2) and Clinical Studies (14.6)].

A randomized, double-blind study in 430 RA patients was conducted in which an endoscopic examination was performed at 6 months. The incidence of endoscopic ulcers in patients taking celecoxib 200 mg twice daily was 4% vs. 15% for patients taking diclofenac SR 75 mg twice daily. However, celecoxib was not statistically different than diclofenac for clinically relevant GI outcomes in the CLASS trial [see Clinical Studies (14.6)].

The incidence of endoscopic ulcers was studied in two 12-week, placebo-controlled studies in 2157 OA and RA patients in whom baseline endoscopies revealed no ulcers. There was no dose relationship for the incidence of gastroduodenal ulcers and the dose of celecoxib (50 mg to 400 mg twice daily). The incidence for naproxen 500 mg twice daily was 16.2% and 17.6% in the two studies, for placebo was 2.0% and 2.3%, and for all doses of celecoxib the incidence ranged between 2.7%–5.9%. There have been no large, clinical outcome studies to compare clinically relevant GI outcomes with celecoxib and naproxen.

In the endoscopic studies, approximately 11% of patients were taking aspirin (≤ 325 mg/day). In the celecoxib groups, the endoscopic ulcer rate appeared to be higher in aspirin users than in non-users. However, the increased rate of ulcers in these aspirin users was less than the endoscopic ulcer rates observed in the active comparator groups, with or without aspirin.

16. HOW SUPPLIED/STORAGE AND HANDLING

VYSCOXA (celecoxib) oral suspension, 10 mg/mL celecoxib is a white, opaque, unflavored suspension, supplied as:

NDC Number | Size
15370-501-16 | 473 mL Bottle

Storage

Store at 20°C to 25°C (68°F to 77°F); excursions permitted between 15°C to 30°C (59°F to 86°F) [see USP Controlled Room Temperature]. Protect from Light. Shake well before use. Discard 21 days after opening.

17. PATIENT COUNSELING INFORMATION

Advise the patient to read the FDA-approved patient labeling (Medication Guide) that accompanies each prescription dispensed. Inform patients, families, or their caregivers of the following information before initiating therapy with VYSCOXA and periodically during the course of ongoing therapy.

Significant Food Effect

Counsel patients that they must take VYSCOXA on an empty stomach and, if there are tolerability issues, to discontinue use of VYSCOXA. Do not advise patients to take VYSCOXA with food.

Cardiovascular Thrombotic Events

Advise patients to be alert for the symptoms of cardiovascular thrombotic events, including chest pain, shortness of breath, weakness, or slurring of speech, and to report any of these symptoms to their health care provider immediately [see Warnings and Precautions (5.1)].

Gastrointestinal Bleeding, Ulceration, and Perforation

Advise patients to report symptoms of ulcerations and bleeding, including epigastric pain, dyspepsia, melena, and hematemesis to their health care provider. In the setting of concomitant use of low-dose aspirin for cardiac prophylaxis, inform patients of the increased risk for and the signs and symptoms of GI bleeding [see Warnings and Precautions (5.2)].

Hepatotoxicity

Inform patients of the warning signs and symptoms of hepatotoxicity (e.g., nausea, fatigue, lethargy, pruritus, diarrhea jaundice, right upper quadrant tenderness, and "flu-like" symptoms). If these occur, instruct patients to stop VYSCOXA and seek immediate medical therapy [see Warnings and Precautions (5.3), Use in Specific Populations (8.6)].

Heart Failure and Edema

Advise patients to be alert for the symptoms of congestive heart failure including shortness of breath, unexplained weight gain, or edema and to contact their healthcare provider if such symptoms occur [see Warnings and Precautions (5.5)].

Anaphylactic Reactions

Inform patients of the signs of an anaphylactic reaction (e.g., difficulty breathing, swelling of the face or throat). Instruct patients to seek immediate emergency help if these occur [see Contraindications (4) and Warnings and Precautions (5.7)].

Serious Skin Reactions, including DRESS

Advise patients to stop taking VYSCOXA immediately if they develop any type of rash or fever and to contact their healthcare provider as soon as possible [see Warnings and Precautions (5.9, 5.10)].

Female Fertility

Advise females of reproductive potential who desire pregnancy that NSAIDs, including VYSCOXA, may be associated with a reversible delay in ovulation [see Use in Specific Populations (8.3)].

Fetal Toxicity

Inform pregnant women to avoid use of VYSCOXA and other NSAIDs starting at 30 weeks of gestation because of the risk of the premature closing of the fetal ductus arteriosus. If treatment with VYSCOXA is needed for a pregnant woman between about 20 to 30 weeks gestation, advise her that she may need to be monitored for oligohydramnios, if treatment continues for longer than 48 hours [see Warnings and Precautions (5.11) and Use in Specific Populations (8.1)].

Avoid Concomitant Use of NSAIDs

Inform patients that the concomitant use of VYSCOXA with other NSAIDs or salicylates (e.g., diflunisal, salsalate) is not recommended due to the increased risk of gastrointestinal toxicity, and little or no increase in efficacy [see Warnings and Precautions (5.2) and Drug Interactions (7)]. Alert patients that NSAIDs may be present in "over the counter" medications for treatment of colds, fever, or insomnia.

Use of NSAIDS and Low-Dose Aspirin

Inform patients not to use low-dose aspirin concomitantly with VYSCOXA until they talk to their healthcare provider [see Drug Interactions (7)].

Manufactured for and Distributed by:
Carwin Pharmaceutical Associates, LLC
Hazlet, NJ 07730

Medication Guide
VYSCOXA™(vis kak sə)
(celecoxib)
oral suspension

VYSCOXA is a prescription medicine that contains celecoxib (a nonsteroidal anti-inflammatory drug [NSAID]). Do not take VYSCOXA with food. VYSCOXA must be taken on an empty stomach at least 2 hours before or 1 hour after food. If you cannot tolerate VYSCOXA on an empty stomach, stop taking VYSCOXA and tell your healthcare provider.

What is the most important information I should know about VYSCOXA, and medicines called nonsteroidal anti-inflammatory drugs (NSAIDs)?
VYSCOXA may cause serious side effects, including:

- Increased risk of a heart attack or stroke that can lead to death. This risk may happen early in treatment and may increase:
  - with increasing doses of NSAIDs
  - with longer use of NSAIDs

Do not take VYSCOXA right before or after a heart surgery called a “coronary artery bypass graft (CABG)".
Avoid taking VYSCOXA after a recent heart attack, unless your healthcare provider tells you to. You may have an increased risk of another heart attack if you take VYSCOXA after a recent heart attack.

- Increased risk of bleeding, ulcers, and tears (perforation) of the esophagus (tube leading from the mouth to the stomach), stomach and intestines:
  - anytime during use
  - without warning symptoms
  - that may cause death

- The risk of getting an ulcer or bleeding increases with:
  - history of stomach ulcers, or stomach or intestinal bleeding with use of NSAIDs
  - taking medicines called “corticosteroids”, “antiplatelet drugs”, “anticoagulants”, “selective serotonin reuptake inhibitors (SSRIs)”, or “serotonin norepinephrine reuptake inhibitors (SNRIs)”

- increasing doses of NSAIDs
- longer use of NSAIDs
- smoking
- drinking alcohol

- older age
- poor health
- advanced liver disease
- bleeding problems

- VYSCOXA should only be used:
  - exactly as prescribed
  - at the lowest dose possible for your treatment
  - for the shortest time needed

What is VYSCOXA?
VYSCOXA is a prescription medicine used:

- for management of the signs and symptoms of osteoarthritis in adults
- for management of the signs and symptoms of rheumatoid arthritis in adults
- for management of the signs and symptoms of ankylosing spondylitis in adults
- for management of the signs and symptoms of juvenile rheumatoid arthritis (JRA) in children 2 years of age and older

VYSCOXA is not used for management of the signs and symptoms of short-term pain or treatment of menstrual cramps.
It is not known if VYSCOXA is safe and effective in children with JRA less than 2 years of age, with a body weight less than 22 pounds (10 kg), and with active signs and symptoms.
It is not known if VYSCOXA is safe and effective in children with osteoarthritis or ankylosing spondylitis.

Do not take VYSCOXA:

- if you are allergic to celecoxib or to any of the ingredients in VYSCOXA. See the end of this Medication Guide for a complete list of ingredients in VYSCOXA.
- if you have had an asthma attack, hives, or other allergic reaction after taking aspirin or any other NSAIDs
- right before or after heart bypass surgery
- if you have a history of allergic reactions to sulfonamides medicines. Ask your healthcare provider if you are not sure.

Before taking VYSCOXA tell your healthcare provider about all of your medical conditions, including if you:

- have heart problems
- have bleeding problems
- have had ulcers
- have liver or kidney problems
- have high blood pressure
- have asthma
- are pregnant or plan to become pregnant. Taking VYSCOXA at about 20 weeks of pregnancy or later may harm your unborn baby. If you need to take VYSCOXA for more than 2 days when you are between 20 and 30 weeks of pregnancy, your healthcare provider may need to monitor the amount of fluid in your womb around your baby. You should not take VYSCOXA after about 30 weeks of pregnancy.
- are breastfeeding or plan to breastfeed. Talk to your healthcare provider about the best way to feed your baby during treatment with VYSCOXA.

Tell your healthcare provider about all of the medicines you or your child take, including prescription or over-the-counter medicines, vitamins or herbal supplements.
VYSCOXA and some other medicines can interact with each other and cause serious side effects.
Do not start taking any new medicine without talking to your healthcare provider first.

How should I take VYSCOXA?

- Take VYSCOXA exactly as your healthcare provider tells you to take it.
- If you take too much VYSCOXA, call your healthcare provider or Poison Control Center at 1-800-222-1222, or go to the nearest hospital emergency room right away.

What are the possible side effects of VYSCOXA?
VYSCOXA can cause serious side effects, including:
See “What is the most important information I should know about VYSCOXA, and medicines called Nonsteroidal Anti-inflammatory Drugs (NSAIDs)?”

- liver problems including liver failure
- new or worse high blood pressure
- heart failure
- kidney problems including kidney failure
- increase in blood potassium level (hyperkalemia)
- life-threatening allergic reactions
- asthma attacks in people who have asthma
- low red blood cells (anemia)
- life-threatening skin reactions
- Other side effects of VYSCOXA include stomach pain, constipation, diarrhea, indigestion, nausea, vomiting, dizziness and rash.

Get emergency help right away if you get any of the following symptoms:

- shortness of breath or trouble breathing
- chest pain
- weakness in one part or side of your body

- slurred speech
- swelling of the face or throat

Stop taking your VYSCOXA and call your healthcare provider right away if you get any of the following symptoms:

- nausea
- more tired or weaker than usual
- diarrhea
- itching
- your skin or eyes look yellow
- indigestion or stomach pain
- flu-like symptoms

- vomit blood
- there is blood in your bowel movement or it is black and sticky like tar
- unusual weight gain
- skin rash or blisters with fever
- swelling of the arms, legs, hands and feet

These are not all the possible side effects of VYSCOXA. Call your doctor for medical advice about side effects. You may report side effects to FDA at 1-800-FDA-1088.

Other information about NSAIDs

- Aspirin is an NSAID but it does not increase the chance of a heart attack. Aspirin can cause bleeding in the brain, stomach, and intestines. Aspirin can also cause ulcers in the stomach and intestines.
- Some NSAIDs are sold in lower doses without a prescription (over-the counter). Talk to your healthcare provider before using over-the-counter NSAIDs for more than 10 days.

How should I store VYSCOXA?

- Store VYSCOXA at room temperature between 68°F to 77°F (20°C to 25°C).
- Keep the VYSCOXA bottles tightly closed and away from light. Shake the bottle well before use.
- Throw (discard) the VYSCOXA bottle away 21 days after opening.

Keep VYSCOXA and all medicines out of the reach of children.

General information about the safe and effective use of VYSCOXA.

Medicines are sometimes prescribed for purposes other than those listed in a Medication Guide. Do not use VYSCOXA for a condition for which it was not prescribed. Do not give VYSCOXA to other people, even if they have the same symptoms that you have. It may harm them. You can ask your pharmacist or healthcare provider for information about VYSCOSA that is written for health professionals.

What are the ingredients in VYSCOXA?

Active ingredient: celecoxib

Inactive ingredients: anhydrous citric acid, glycerin, magnesium aluminometasilicate, methylparaben, propylparaben, purified water, sodium citrate dihydrate, sucralose, and xanthan gum.

Manufactured for and Distributed by: Carwin Pharmaceutical Associates, LLC, Hazlet, NJ 07730

For more information, go to www.carwinpharma.com or call: 844-700-5011

This Medication Guide has been approved by the U.S. Food and Drug Administration.

Issued: 07/2025